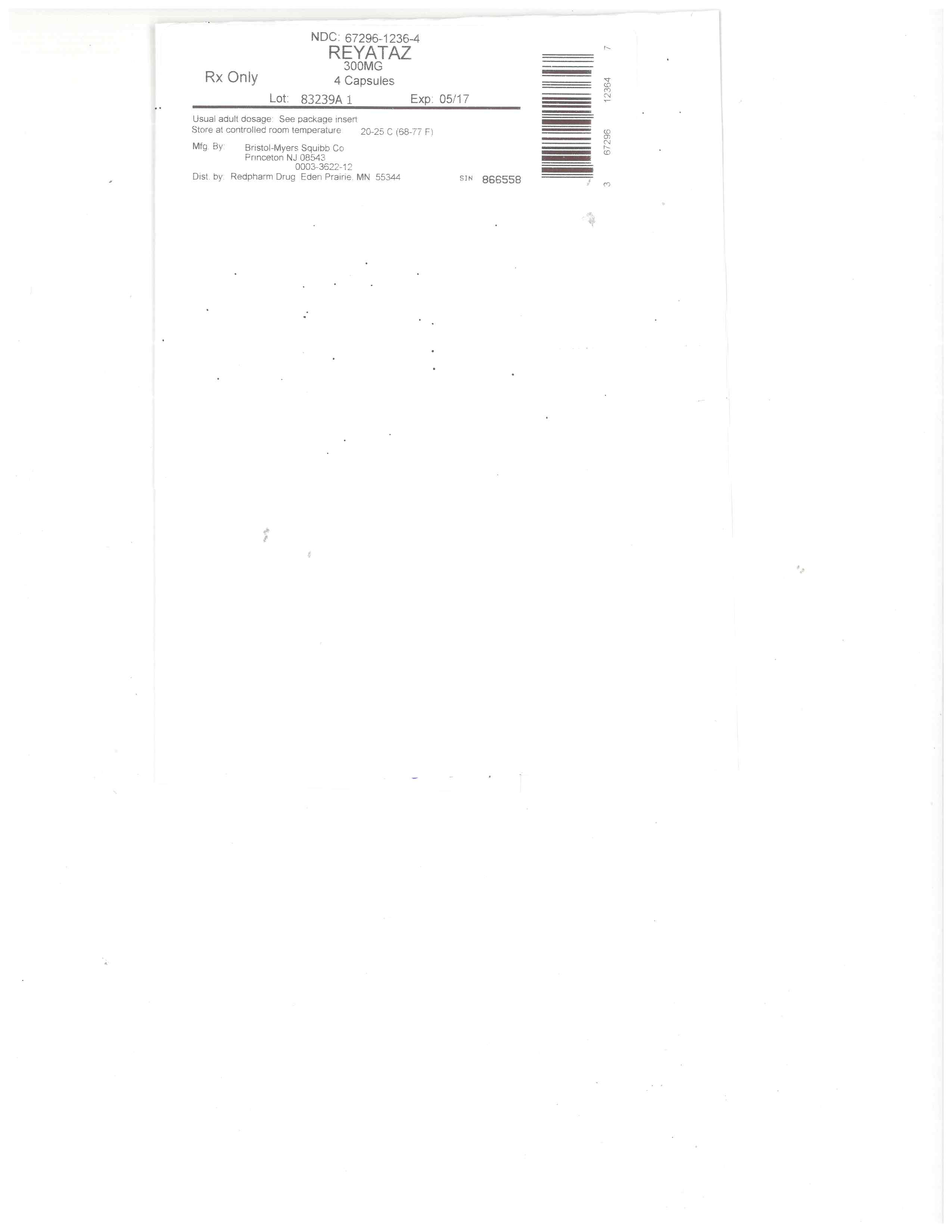 DRUG LABEL: REYATAZ
NDC: 67296-1236 | Form: CAPSULE, GELATIN COATED
Manufacturer: RedPharm Drug, Inc.
Category: prescription | Type: HUMAN PRESCRIPTION DRUG LABEL
Date: 20220120

ACTIVE INGREDIENTS: ATAZANAVIR SULFATE 300 mg/1 1
INACTIVE INGREDIENTS: CROSPOVIDONE (15 MPA.S AT 5%); FERRIC OXIDE YELLOW; ISOPROPYL ALCOHOL; AMMONIA; BUTYL ALCOHOL; FERROSOFERRIC OXIDE; SHELLAC; LACTOSE MONOHYDRATE; MAGNESIUM STEARATE; GELATIN; FD&C BLUE NO. 2; TITANIUM DIOXIDE; FERRIC OXIDE RED; PROPYLENE GLYCOL; ALCOHOL

HIGHLIGHTS OF PRESCRIBING INFORMATION

These highlights do not include all the information needed to use REYATAZ safely and effectively. See full prescribing information for REYATAZ.
REYATAZ ® (atazanavir) capsules, for oral use
REYATAZ ® (atazanavir) oral powder
Initial U.S. Approval: 2003

RECENT MAJOR CHANGES

Indications and Usage (1) 9/2015
Dosage and Administration,
Overview (2.1) 9/2015
Dosage and Administration of REYATAZ
Oral Powder in Pediatric Patients (2.4) 9/2015
Contraindications (4) 9/2016

INDICATIONS AND USAGE

REYATAZ is a protease inhibitor indicated for use in combination with other antiretroviral agents for the treatment of HIV-1 infection for patients 3 months and older weighing at least 5 kg. (1)

DOSAGE AND ADMINISTRATION

•
Treatment-naive adults: REYATAZ 300 mg with ritonavir 100 mg once daily with food or REYATAZ 400 mg once daily with food. (2.2)
•
Treatment-experienced adults: REYATAZ 300 mg with ritonavir 100 mg once daily with food. (2.2)
•
Pediatric patients: REYATAZ capsule dosage is based on body weight not to exceed the adult dose and must be taken with food. (2.3)
•
REYATAZ oral powder: Must be taken with ritonavir and food and should not be used in pediatric patients who weigh less than 5 kg. (2.4)
•
Pregnancy: REYATAZ 300 mg with ritonavir 100 mg once daily with food, with dosing modifications for some concomitant medications. (2.5)
•
Dosing modifications: may be required for concomitant therapy (2.2, 2.3, 2.4, 2.5), renal impairment(2.6), and hepatic impairment (2.7).

DOSAGE FORMS AND STRENGTHS

•
Capsules: 150 mg, 200 mg, 300 mg. (3, 16)
•
Oral powder: 50 mg packet. (3, 16)

CONTRAINDICATIONS

•
REYATAZ is contraindicated in patients with previously demonstrated hypersensitivity (eg, Stevens-Johnson syndrome, erythema multiforme, or toxic skin eruptions) to any of the components of this product. (4)
•
Coadministration with alfuzosin, triazolam, orally administered midazolam, ergot derivatives, rifampin, irinotecan, lurasidone (if REYATAZ is coadministered with ritonavir), lovastatin, simvastatin, indinavir, cisapride, pimozide, St. John’s wort, nevirapine, and sildenafil when dosed as REVATIO ®. (4)

WARNINGS AND PRECAUTIONS

•
Cardiac conduction abnormalities: PR interval prolongation may occur in some patients. ECG monitoring should be considered in patients with preexisting conduction system disease or when administered with other drugs that may prolong the PR interval. (5.1, 7.3, 12.2, 17)
•
Severe Skin Reactions: Discontinue if severe rash develops. (5.2, 17)
•
Hyperbilirubinemia: Most patients experience asymptomatic increases in indirect bilirubin, which is reversible upon discontinuation. Do not dose reduce. If a concomitant transaminase increase occurs, evaluate for alternative etiologies. (5.3)
•
Phenylketonuria: REYATAZ oral powder contains phenylalanine which can be harmful to patients with phenylketonuria. (5.4)
•
Hepatotoxicity: Patients with hepatitis B or C infection are at risk of increased transaminases or hepatic decompensation. Monitor hepatic laboratory tests prior to therapy and during treatment.(2.7, 5.5, 8.8)
•
Nephrolithiasis and cholelithiasis have been reported. Consider temporary interruption or discontinuation. (5.6)
•
The concomitant use of REYATAZ/ritonavir and certain other medications may result in known or potentially significant drug interactions. Consult the full prescribing information prior to and during treatment for potential drug interactions. (5.7, 7.3)
•
Patients receiving REYATAZ may develop new onset or exacerbations of diabetes mellitus/hyperglycemia (5.8), immune reconstitution syndrome (5.9), and redistribution/accumulation of body fat (5.10).
•
Hemophilia: Spontaneous bleeding may occur and additional factor VIII may be required. (5.11)

ADVERSE REACTIONS

Most common adverse reactions (≥2%) are nausea, jaundice/scleral icterus, rash, headache, abdominal pain, vomiting, insomnia, peripheral neurologic symptoms, dizziness, myalgia, diarrhea, depression, and fever. (6.1)

To report SUSPECTED ADVERSE REACTIONS, contact Bristol-Myers Squibb at 1-800-721-5072 or FDA at 1-800-FDA-1088 or WWW.FDA.GOV/MEDWATCH.

DRUG INTERACTIONS

Coadministration of REYATAZ can alter the concentration of other drugs and other drugs may alter the concentration of atazanavir. The potential drug-drug interactions must be considered prior to and during therapy. (4, 7, 12.3)

USE IN SPECIFIC POPULATIONS

•
Pregnancy: Available human and animal data suggest that atazanavir does not increase the risk of major birth defects overall compared to the background rate. (8.1)
•
Lactation: Breastfeeding is not recommended. (8.2)
•
Hepatitis B or C co-infection: Monitor liver enzymes. (5.5, 6.1)
•
Renal impairment: REYATAZ is not recommended for use in treatment-experienced patients with end stage renal disease managed with hemodialysis. (2.6, 8.7)
•
Hepatic impairment: REYATAZ is not recommended in patients with severe hepatic impairment. REYATAZ/ritonavir is not recommended in patients with any degree of hepatic impairment. (2.7, 8.8)

See 17 for PATIENT COUNSELING INFORMATION and FDA-approved patient labeling.

Revised: 9/2016

FULL PRESCRIBING INFORMATION: CONTENTS*

1 INDICATIONS AND USAGE
2 DOSAGE AND ADMINISTRATION
2.1 Overview
2.2 Dosage of REYATAZ in Adult Patients
2.3 Dosage of REYATAZ Capsules in Pediatric Patients
2.4 Dosage and Administration of REYATAZ Oral Powder in Pediatric Patients
2.5 Dosage Adjustments in Pregnant Patients
2.6 Dosage in Patients with Renal Impairment
2.7 Dosage Adjustments in Patients with Hepatic Impairment
3 DOSAGE FORMS AND STRENGTHS
4 CONTRAINDICATIONS
5 WARNINGS AND PRECAUTIONS
5.1 Cardiac Conduction Abnormalities
5.2 Severe Skin Reactions
5.3 Hyperbilirubinemia
5.4 Patients with Phenylketonuria
5.5 Hepatotoxicity
5.6 Nephrolithiasis and Cholelithiasis
5.7 Risk of Serious Adverse Reactions Due to Drug Interactions
5.8 Diabetes Mellitus/Hyperglycemia
5.9 Immune Reconstitution Syndrome
5.10 Fat Redistribution
5.11 Hemophilia
5.12 Resistance/Cross-Resistance
6 ADVERSE REACTIONS
6.1 Clinical Trial Experience
6.2 Postmarketing Experience
7 DRUG INTERACTIONS
7.1 Potential for REYATAZ to Affect Other Drugs
7.2 Potential for Other Drugs to Affect REYATAZ
7.3 Established and Other Potentially Significant Drug Interactions
7.4 Drugs with No Observed Interactions with REYATAZ
8 USE IN SPECIFIC POPULATIONS
8.1 Pregnancy
8.2 Lactation
8.4 Pediatric Use
8.5 Geriatric Use
8.6 Age/Gender
8.7 Impaired Renal Function
8.8 Impaired Hepatic Function
10 OVERDOSAGE
11 DESCRIPTION
12 CLINICAL PHARMACOLOGY
12.1 Mechanism of Action
12.2 Pharmacodynamics
12.3 Pharmacokinetics
12.4 Microbiology
13 NONCLINICAL TOXICOLOGY
13.1 Carcinogenesis, Mutagenesis, Impairment of Fertility
14 CLINICAL STUDIES
14.1 Adult Patients without Prior Antiretroviral Therapy
14.2 Adult Patients with Prior Antiretroviral Therapy
14.3 Pediatric Patients
16 HOW SUPPLIED/STORAGE AND HANDLING
17 PATIENT COUNSELING INFORMATION

*
Sections or subsections omitted from the full prescribing information are not listed.

1 INDICATIONS AND USAGE

REYATAZ® (atazanavir) is indicated in combination with other antiretroviral agents for the treatment of HIV-1 infection for patients 3 months and older weighing at least 5 kg.

Limitations of Use:

•
REYATAZ is not recommended for use in pediatric patients below the age of 3 months due to the risk of kernicterus.
•
Use of REYATAZ/ritonavir in treatment-experienced patients should be guided by the number of baseline primary protease inhibitor resistance substitutions [see MICROBIOLOGY (12.4)].

2 DOSAGE AND ADMINISTRATION

2.1 Overview

•
REYATAZ capsules and oral powder must be taken with food.
•
Do not open the capsules.
•
The recommended oral dosage of REYATAZ depends on the treatment history of the patient and the use of other coadministered drugs. When coadministered with H 2-receptor antagonists or proton-pump inhibitors, dose separation may be required [see DOSAGE AND ADMINISTRATION (2.2, 2.3, 2.4, 2.5) and DRUG INTERACTIONS (7)].
•
REYATAZ capsules without ritonavir are not recommended for treatment-experienced adult or pediatric patients with prior virologic failure [see CLINICAL STUDIES (14)].
•
REYATAZ oral powder must be taken with ritonavir and is not recommended for use in children who weigh less than 5 kg [see DOSAGE AND ADMINISTRATION (2.4)].
•
Efficacy and safety of REYATAZ with ritonavir when ritonavir is administered in doses greater than 100 mg once daily have not been established. The use of higher ritonavir doses may alter the safety profile of atazanavir (cardiac effects, hyperbilirubinemia) and, therefore, is not recommended. Prescribers should consult the complete prescribing information for ritonavir when using ritonavir.

2.2 Dosage of REYATAZ in Adult Patients

Table 1 displays the recommended dosage of REYATAZ capsules in treatment-naive and treatment-experienced adults. Table 1 also displays recommended dosage of REYATAZ and ritonavir when given concomitantly with other antiretroviral drugs and H2-receptor antagonists (H2RA). Ritonavir is required with several REYATAZ dosage regimens (see the ritonavir complete prescribing information about the safe and effective use of ritonavir). The use of REYATAZ in treatment-experienced adult patients without ritonavir is not recommended.

Table 1: Recommended REYATAZ and Ritonavir Dosage in Adultsa,b
a See DRUG INTERACTIONS (7) for instructions concerning coadministration of acid reducing medications (eg, H2RA or proton pump inhibitors [PPIs]), and other antiretroviral drugs (eg, efavirenz, tenofovir, and didanosine).
b For adult patients who cannot swallow the capsules, REYATAZ oral powder is taken once daily with food at the same recommended adult dosage as the capsules along with ritonavir.

REYATAZ Once Daily
Dosage

Ritonavir Once Daily
Dosage

Treatment-Naive Adult Patients

recommended regimen

300 mg

100 mg

unable to tolerate ritonavir

400 mg

N/A

in combination with efavirenz

400 mg

100 mg

Treatment-Experienced Adult Patients

recommended regimen

300 mg

100 mg

in combination with both H2RA and tenofovir

400 mg

100 mg

2.3 Dosage of REYATAZ Capsules in Pediatric Patients

The recommended daily dosage of REYATAZ capsules and ritonavir in pediatric patients (6 years of age to less than 18 years of age) is based on body weight (see Table 2).

Table 2: Recommended Dosage of REYATAZ Capsules and Ritonavir in Pediatric Patients (6 to less than 18 years of age)a,b
a Administer REYATAZ capsules and ritonavir simultaneously with food.
b The same recommendations regarding the timing and maximum doses of concomitant PPIs and H2RAs in adults also apply to pediatric patients. See DRUG INTERACTIONS (7) for instructions concerning coadministration of acid reducing medications (eg, H2RA or PPIs), and other antiretroviral drugs (eg, efavirenz, tenofovir, and didanosine).
c In treatment-experienced patients, REYATAZ capsules must be administered with ritonavir.

Body weight

REYATAZ Daily Dosage

Ritonavir Daily Dosage

Treatment-Naive and Treatment-Experiencedc

Less than 15 kg

Capsules not recommended

N/A

15 kg to less than 20 kg

150 mg

100 mg

20 kg to less than 40 kg

200 mg

100 mg

At least 40 kg

300 mg

100 mg

Treatment-Naive, at least 13 years old and cannot tolerate ritonavirc

At least 40 kg

400 mg

N/A

2.4 Dosage and Administration of REYATAZ Oral Powder in Pediatric Patients

REYATAZ oral powder is for use in treatment-naive or treatment-experienced pediatric patients who are at least 3 months of age and weighing at least 5 kg. REYATAZ oral powder must be mixed with food or beverage for administration and ritonavir must be given immediately afterwards. Table 3 displays the recommended dosage of REYATAZ oral powder and ritonavir.

Table 3: Recommended Dosage of REYATAZ Oral Powder and Ritonavir in Pediatric Patients (at least 3 months of age and weighing at least 5 kg)a,b
a The same recommendations regarding the timing and maximum doses of concomitant PPIs and H2RAs in adults also apply to pediatric patients. See DRUG INTERACTIONS (7) for instructions concerning coadministration of acid reducing medications (eg, H2RA or PPIs), and other antiretroviral drugs (eg, efavirenz, tenofovir, and didanosine).
b For pediatric patients at least 25 kg who cannot swallow REYATAZ capsules, 300 mg (6 packets) REYATAZ oral powder is taken once daily with food along with 100 mg ritonavir.
c Only patients weighing 5 to less than 10 kg who do not tolerate the 200 mg (4 packets) dose of REYATAZ oral powder and have not previously taken an HIV protease inhibitor, may take 150 mg (3 packets) REYATAZ oral powder with close HIV viral load monitoring.
d Each packet contains 50 mg of REYATAZ.

Body Weight

Daily Dosage of REYATAZ
Oral Powder

Daily Dosage of Ritonavir
Oral Solution

5 kg to less than 15 kg

200 mg (4 packets)c,d

80 mg

15 kg to less than 25 kg

250 mg (5 packets)d

80 mg

Instructions for Mixing REYATAZ Oral Powder [see FDA-approved Instructions for Use]

•
Determine the number of packets (3, 4, 5 or 6 packets) that are needed.
•
Prior to mixing, tap the packet to settle the powder.
•
It is preferable to mix REYATAZ oral powder with food such as applesauce or yogurt. Mixing REYATAZ oral powder with a beverage (milk, infant formula, or water) may be used for infants who can drink from a cup. For young infants (less than 6 months) who cannot eat solid food or drink from a cup, REYATAZ oral powder should be mixed with infant formula and given using an oral dosing syringe. Administration of REYATAZ and infant formula using an infant bottle is not recommended because full dose may not be delivered.
•
Use a clean pair of scissors to cut each packet along the dotted line.
•
Mixing with food: Using a spoon, mix the recommended number of REYATAZ oral powder packets with a minimum of one tablespoon of food (such as applesauce or yogurt). Feed the mixture to the infant or young child. Add an additional one tablespoon of food to the small container, mix, and feed the child the residual mixture.
•
Mixing with a beverage such as milk or water in a small drinking cup: Using a spoon, mix the recommended number of REYATAZ oral powder packets with a minimum of 30 mL of the beverage. Have the child drink the mixture. Add an additional 15 mL more of beverage to the drinking cup, mix, and have the child drink the residual mixture. If water is used, food should also be taken at the same time.
•
Mixing with liquid infant formula using an oral dosing syringe and a small medicine cup: Using a spoon, mix the recommended number of REYATAZ oral powder packets with 10 mL of prepared liquid infant formula. Draw up the full amount of the mixture into an oral syringe and administer into either right or left inner cheek of infant. Pour another 10 mL of formula into the medicine cup to rinse off remaining REYATAZ oral powder in cup. Draw up residual mixture into the syringe and administer into either right or left inner cheek of infant.
•
Administer ritonavir immediately following REYATAZ powder administration.
•
Administer the entire dosage of REYATAZ oral powder (mixed in the food or beverage) within one hour of preparation (may leave the mixture at room temperature during this one hour period). Ensure that the patient eats or drinks all the food or beverage that contains the powder. Additional food may be given after consumption of the entire mixture.

2.5 Dosage Adjustments in Pregnant Patients

Table 4 includes the recommended dosage of REYATAZ capsules and ritonavir in treatment-naive and treatment-experienced pregnant patients. In these patients, REYATAZ must be administered with ritonavir. There are no dosage adjustments for postpartum patients (see Table 1 for the recommended REYATAZ dosage in adults). [See USE IN SPECIFIC POPULATIONS (8.1).]

Table 4: Recommended Dosage of REYATAZ and Ritonavir in Pregnant Patientsa
a See DRUG INTERACTIONS (7) for instructions concerning coadministration of acid reducing medications (eg, H2RA or PPIs), and other antiretroviral drugs (eg, efavirenz, tenofovir, and didanosine).
b REYATAZ is not recommended for treatment-experienced pregnant patients during the second and third trimester taking REYATAZ with both tenofovir and H2RA.

REYATAZ
Once Daily
Dosage

Ritonavir
Once Daily
Dosage

Treatment-Naive and Treatment-Experienced

Recommended Regimen

300 mg

100 mg

Treatment-Experienced During the Second or Third Trimester When Coadministered with either H2RA or Tenofovirb

In combination with either H2RA or tenofovir

400 mg

100 mg

2.6 Dosage in Patients with Renal Impairment

For patients with renal impairment, including those with severe renal impairment who are not managed with hemodialysis, no dose adjustment is required for REYATAZ. Treatment-naive patients with end stage renal disease managed with hemodialysis should receive REYATAZ 300 mg with ritonavir 100 mg. REYATAZ is not recommended in HIV-treatment-experienced patients with end stage renal disease managed with hemodialysis. [See USE IN SPECIFIC POPULATIONS (8.7).]

2.7 Dosage Adjustments in Patients with Hepatic Impairment

Table 5 displays the recommended REYATAZ dosage in treatment-naive patients with hepatic impairment. The use of REYATAZ in patients with severe hepatic impairment (Child-Pugh Class C) is not recommended. The coadministration of REYATAZ with ritonavir in patients with any degree of hepatic impairment is not recommended.

Table 5: Recommended Dosage of REYATAZ Capsules in Treatment-Naive Adults with Hepatic Impairment

REYATAZ Once Daily Dosage

Mild hepatic impairment (Child-Pugh Class A)

400 mg

Moderate hepatic impairment (Child-Pugh Class B)

300 mg

Severe hepatic impairment (Child-Pugh Class C)

REYATAZ with or without ritonavir is not recommended

3 DOSAGE FORMS AND STRENGTHS

REYATAZ Capsules:

•
150 mg capsule with blue cap and powder blue body, printed with white ink “BMS 150 mg” on the cap and with blue ink “3624” on the body.
•
200 mg capsule with blue cap and blue body, printed with white ink “BMS 200 mg” on the cap and with white ink “3631” on the body.
•
300 mg capsule with red cap and blue body, printed with white ink “BMS 300 mg” on the cap and with white ink “3622” on the body.

REYATAZ Oral Powder:

•
50 mg of atazanavir as an oral powder in a packet.

4 CONTRAINDICATIONS

REYATAZ is contraindicated:

•
in patients with previously demonstrated clinically significant hypersensitivity (eg, Stevens-Johnson syndrome, erythema multiforme, or toxic skin eruptions) to any of the components of REYATAZ capsules or REYATAZ oral powder [see WARNINGS AND PRECAUTIONS (5.2)].
•
when coadministered with drugs that are highly dependent on CYP3A or UGT1A1 for clearance, and for which elevated plasma concentrations of the interacting drugs are associated with serious and/or life-threatening events (see Table 6).
•
when coadministered with drugs that strongly induce CYP3A and may lead to lower exposure and loss of efficacy of REYATAZ (see Table 6).

Table 6 displays drugs that are contraindicated with REYATAZ.

Table 6: Drugs that are Contraindicated with REYATAZ (Information in the table applies to REYATAZ with or without ritonavir, unless otherwise indicated)
a See DRUG INTERACTIONS, TABLE 16 (7) for parenterally administered midazolam.
b See DRUG INTERACTIONS, TABLE 16 (7) for sildenafil when dosed as VIAGRA® for erectile dysfunction.

Drug Class

Drugs within class that are contraindicated with REYATAZ

Clinical Comment

Alpha 1-Adrenoreceptor Antagonist

Alfuzosin

Potential for increased alfuzosin concentrations, which can result in hypotension.

Antimycobacterials

Rifampin

Rifampin substantially decreases plasma concentrations of atazanavir, which may result in loss of therapeutic effect and development of resistance.

Antineoplastics

Irinotecan

Atazanavir inhibits UGT1A1 and may interfere with the metabolism of irinotecan, resulting in increased irinotecan toxicities.

Antipsychotics

Lurasidone

Potential for serious and/or life-threatening reactions if REYATAZ is coadministered with ritonavir.

Pimozide

Potential for serious and/or life-threatening reactions such as cardiac arrhythmias.

Benzodiazepines

Triazolam, orally administered midazolama

Triazolam and orally administered midazolam are extensively metabolized by CYP3A4. Coadministration of triazolam or orally administered midazolam with REYATAZ may cause large increases in the concentration of these benzodiazepines. Potential for serious and/or life-threatening events such as prolonged or increased sedation or respiratory depression.

Ergot Derivatives

Dihydroergotamine, ergotamine, ergonovine, methylergonovine

Potential for serious and/or life-threatening events such as acute ergot toxicity characterized by peripheral vasospasm and ischemia of the extremities and other tissues.

GI Motility Agent

Cisapride

Potential for serious and/or life-threatening reactions such as cardiac arrhythmias.

Herbal Products

St. John’s wort (Hypericum perforatum)

Coadministration of St. John’s wort and REYATAZ may result in loss of therapeutic effect and development of resistance.

HMG-CoA Reductase Inhibitors

Lovastatin, simvastatin

Potential for serious reactions such as myopathy, including rhabdomyolysis.

PDE5 Inhibitor

Sildenafilb when dosed as REVATIO® for the treatment of pulmonary arterial hypertension

Potential for sildenafil-associated adverse events (which include visual disturbances, hypotension, priapism, and syncope).

Protease Inhibitors

Indinavir

Both REYATAZ and indinavir are associated with indirect (unconjugated) hyperbilirubinemia.

Non-nucleoside Reverse Transcriptase Inhibitors

Nevirapine

Nevirapine substantially decreases atazanavir exposure which may result in loss of therapeutic effect and development of resistance. Potential risk for nevirapine-associated adverse reactions due to increased nevirapine exposures.

Table 6: Drugs that are Contraindicated with REYATAZ (Information in the table applies to REYATAZ with or without ritonavir, unless otherwise indicated)
a See DRUG INTERACTIONS, TABLE 16 (7) for parenterally administered midazolam.
b See DRUG INTERACTIONS, TABLE 16 (7) for sildenafil when dosed as VIAGRA® for erectile dysfunction.

5 WARNINGS AND PRECAUTIONS

5.1 Cardiac Conduction Abnormalities

REYATAZ has been shown to prolong the PR interval of the electrocardiogram in some patients. In healthy volunteers and in patients, abnormalities in atrioventricular (AV) conduction were asymptomatic and generally limited to first-degree AV block. There have been reports of second-degree AV block and other conduction abnormalities [see ADVERSE REACTIONS (6.2) and OVERDOSAGE (10)]. In clinical trials that included electrocardiograms, asymptomatic first-degree AV block was observed in 5.9% of atazanavir-treated patients (n=920), 5.2% of lopinavir/ritonavir-treated patients (n=252), 10.4% of nelfinavir-treated patients (n=48), and 3.0% of efavirenz-treated patients (n=329). In Study AI424-045, asymptomatic first-degree AV block was observed in 5% (6/118) of atazanavir/ritonavir-treated patients and 5% (6/116) of lopinavir/ritonavir-treated patients who had on-study electrocardiogram measurements. Because of limited clinical experience in patients with preexisting conduction system disease (eg, marked first-degree AV block or second- or third-degree AV block). ECG monitoring should be considered in these patients. [See CLINICAL PHARMACOLOGY (12.2).]

5.2 Severe Skin Reactions

In controlled clinical trials, rash (all grades, regardless of causality) occurred in approximately 20% of patients treated with REYATAZ. The median time to onset of rash in clinical studies was 7.3 weeks and the median duration of rash was 1.4 weeks. Rashes were generally mild-to-moderate maculopapular skin eruptions. Treatment-emergent adverse reactions of moderate or severe rash (occurring at a rate of ≥2%) are presented for the individual clinical studies [see ADVERSE REACTIONS (6.1)]. Dosing with REYATAZ was often continued without interruption in patients who developed rash. The discontinuation rate for rash in clinical trials was <1%. Cases of Stevens-Johnson syndrome, erythema multiforme, and toxic skin eruptions, including drug rash, eosinophilia, and systemic symptoms (DRESS) syndrome, have been reported in patients receiving REYATAZ. [See CONTRAINDICATIONS (4) and ADVERSE REACTIONS (6.1).] REYATAZ should be discontinued if severe rash develops.

5.3 Hyperbilirubinemia

Most patients taking REYATAZ experience asymptomatic elevations in indirect (unconjugated) bilirubin related to inhibition of UDP-glucuronosyl transferase (UGT). This hyperbilirubinemia is reversible upon discontinuation of REYATAZ. Hepatic transaminase elevations that occur with hyperbilirubinemia should be evaluated for alternative etiologies. No long-term safety data are available for patients experiencing persistent elevations in total bilirubin >5 times the upper limit of normal (ULN). Alternative antiretroviral therapy to REYATAZ may be considered if jaundice or scleral icterus associated with bilirubin elevations presents cosmetic concerns for patients. Dose reduction of atazanavir is not recommended since long-term efficacy of reduced doses has not been established. [See ADVERSE REACTIONS (6.1).]

5.4 Patients with Phenylketonuria

Phenylalanine can be harmful to patients with phenylketonuria (PKU). REYATAZ oral powder contains phenylalanine (a component of aspartame). Each packet of REYATAZ oral powder contains 35 mg of phenylalanine. REYATAZ capsules do not contain phenylalanine.

5.5 Hepatotoxicity

Patients with underlying hepatitis B or C viral infections or marked elevations in transaminases before treatment may be at increased risk for developing further transaminase elevations or hepatic decompensation. In these patients, hepatic laboratory testing should be conducted prior to initiating therapy with REYATAZ and during treatment. [See ADVERSE REACTIONS (6.1) and USE IN SPECIFIC POPULATIONS (8.8).]

5.6 Nephrolithiasis and Cholelithiasis

Cases of nephrolithiasis and/or cholelithiasis have been reported during postmarketing surveillance in HIV-infected patients receiving REYATAZ therapy. Some patients required hospitalization for additional management and some had complications. Because these events were reported voluntarily during clinical practice, estimates of frequency cannot be made. If signs or symptoms of nephrolithiasis and/or cholelithiasis occur, temporary interruption or discontinuation of therapy may be considered. [See ADVERSE REACTIONS (6.2).]

5.7 Risk of Serious Adverse Reactions Due to Drug Interactions

Initiation of REYATAZ with ritonavir, a CYP3A inhibitor, in patients receiving medications metabolized by CYP3A or initiation of medications metabolized by CYP3A in patients already receiving REYATAZ with ritonavir, may increase plasma concentrations of medications metabolized by CYP3A. Initiation of medications that inhibit or induce CYP3A may increase or decrease concentrations of REYATAZ with ritonavir, respectively. These interactions may lead to:

•
clinically significant adverse reactions potentially leading to severe, life threatening, or fatal events from greater exposures of concomitant medications.
•
clinically significant adverse reactions from greater exposures of REYATAZ with ritonavir.
•
loss of therapeutic effect of REYATAZ with ritonavir and possible development of resistance.

See Table 16 for steps to prevent or manage these possible and known significant drug interactions, including dosing recommendations [see DRUG INTERACTIONS (7)]. Consider the potential for drug interactions prior to and during REYATAZ/ritonavir therapy; review concomitant medications during REYATAZ/ritonavir therapy; and monitor for the adverse reactions associated with the concomitant medications [see CONTRAINDICATIONS (4) and DRUG INTERACTIONS (7)].

5.8 Diabetes Mellitus/Hyperglycemia

New-onset diabetes mellitus, exacerbation of preexisting diabetes mellitus, and hyperglycemia have been reported during postmarketing surveillance in HIV-infected patients receiving protease inhibitor therapy. Some patients required either initiation or dose adjustments of insulin or oral hypoglycemic agents for treatment of these events. In some cases, diabetic ketoacidosis has occurred. In those patients who discontinued protease inhibitor therapy, hyperglycemia persisted in some cases. Because these events have been reported voluntarily during clinical practice, estimates of frequency cannot be made and a causal relationship between protease inhibitor therapy and these events has not been established. [See ADVERSE REACTIONS (6.2).]

5.9 Immune Reconstitution Syndrome

Immune reconstitution syndrome has been reported in patients treated with combination antiretroviral therapy, including REYATAZ. During the initial phase of combination antiretroviral treatment, patients whose immune system responds may develop an inflammatory response to indolent or residual opportunistic infections (such as Mycobacterium avium infection, cytomegalovirus, Pneumocystis jiroveci pneumonia, or tuberculosis), which may necessitate further evaluation and treatment.

Autoimmune disorders (such as Graves’ disease, polymyositis, and Guillain-Barré syndrome) have also been reported to occur in the setting of immune reconstitution; however, the time to onset is more variable, and can occur many months after initiation of treatment.

5.10 Fat Redistribution

Redistribution/accumulation of body fat including central obesity, dorsocervical fat enlargement (buffalo hump), peripheral wasting, facial wasting, breast enlargement, and “cushingoid appearance” have been observed in patients receiving antiretroviral therapy. The mechanism and long-term consequences of these events are currently unknown. A causal relationship has not been established.

5.11 Hemophilia

There have been reports of increased bleeding, including spontaneous skin hematomas and hemarthrosis, in patients with hemophilia type A and B treated with protease inhibitors. In some patients additional factor VIII was given. In more than half of the reported cases, treatment with protease inhibitors was continued or reintroduced. A causal relationship between protease inhibitor therapy and these events has not been established.

5.12 Resistance/Cross-Resistance

Various degrees of cross-resistance among protease inhibitors have been observed. Resistance to atazanavir may not preclude the subsequent use of other protease inhibitors. [See MICROBIOLOGY (12.4).]

6 ADVERSE REACTIONS

The following adverse reactions are discussed in greater detail in other sections of the labeling:

•
cardiac conduction abnormalities [see WARNINGS AND PRECAUTIONS (5.1)]
•
rash [see WARNINGS AND PRECAUTIONS (5.2)]
•
hyperbilirubinemia [see WARNINGS AND PRECAUTIONS (5.3)]
•
nephrolithiasis and cholelithiasis [see WARNINGS AND PRECAUTIONS (5.6)]

Because clinical trials are conducted under widely varying conditions, adverse reaction rates observed in the clinical trials of a drug cannot be directly compared to rates in the clinical trials of another drug and may not reflect the rates observed in practice.

6.1 Clinical Trial Experience

Adverse Reactions in Treatment-Naive Adult Patients

The safety profile of REYATAZ in treatment-naive adults is based on 1625 HIV-1 infected patients in clinical trials. 536 patients received REYATAZ 300 mg with ritonavir 100 mg and 1089 patients received REYATAZ 400 mg or higher (without ritonavir).

The most common adverse reactions were nausea, jaundice/scleral icterus, and rash.

Selected clinical adverse reactions of moderate or severe intensity reported in ≥2% of treatment-naive patients receiving combination therapy including REYATAZ 300 mg with ritonavir 100 mg and REYATAZ 400 mg (without ritonavir) are presented in Tables 7 and 8, respectively.

Table 7: Selected Adverse Reactionsa of Moderate or Severe Intensity Reported in ≥2% of Adult Treatment-Naive Patients,b Study AI424-138
* None reported in this treatment arm.
a Includes events of possible, probable, certain, or unknown relationship to treatment regimen.
b Based on the regimen containing REYATAZ.
c Median time on therapy.
d As a fixed-dose combination: 300 mg tenofovir, 200 mg emtricitabine once daily.

96 weeksc
REYATAZ 300 mg with ritonavir
100 mg (once daily) and tenofovir
with emtricitabined
(n=441)

96 weeksc
lopinavir 400 mg with ritonavir
100 mg (twice daily) and tenofovir
with emtricitabined
(n=437)

Digestive System

Nausea

4%

8%

Jaundice/scleral icterus

5%

*

Diarrhea

2%

12%

Skin and Appendages

Rash

3%

2%

Table 8: Selected Adverse Reactionsa of Moderate or Severe Intensity Reported in ≥2% of Adult Treatment-Naive Patients,b Studies AI424-034, AI424-007, and AI424-008
* None reported in this treatment arm.
a Includes events of possible, probable, certain, or unknown relationship to treatment regimen.
b Based on regimens containing REYATAZ.
c Median time on therapy.
d Includes long-term follow-up.
e As a fixed-dose combination: 150 mg lamivudine, 300 mg zidovudine twice daily.

Study AI424-034

Studies AI424-007, -008

64 weeksc

REYATAZ
400 mg once daily
+ lamivudine +
zidovudinee
(n=404)

64 weeksc

efavirenz
600 mg once daily
+ lamivudine +
zidovudinee
(n=401)

120 weeksc,d

REYATAZ
400 mg once daily
+ stavudine +
lamivudine or
didanosine
(n=279)

73 weeksc,d

nelfinavir
750 mg TID or
1250 mg BID +
stavudine +
lamivudine or
didanosine
(n=191)

Body as a Whole

Headache

6%

6%

1%

2%

Digestive System

Nausea

14%

12%

6%

4%

Jaundice/scleral icterus

7%

*

7%

*

Vomiting

4%

7%

3%

3%

Abdominal pain

4%

4%

4%

2%

Diarrhea

1%

2%

3%

16%

Nervous System

Insomnia

3%

3%

<1%

*

Dizziness

2%

7%

<1%

*

Peripheral neurologic symptoms

<1%

1%

4%

3%

Skin and Appendages

Rash

7%

10%

5%

1%

Adverse Reactions in Treatment-Experienced Adult Patients

The safety profile of REYATAZ in treatment-experienced adults is based on 119 HIV-1 infected patients in clinical trials.

The most common adverse reactions are jaundice/scleral icterus and myalgia.

Selected clinical adverse reactions of moderate or severe intensity reported in ≥2% of treatment-experienced patients receiving REYATAZ/ritonavir are presented in Table 9.

Table 9: Selected Adverse Reactionsa of Moderate or Severe Intensity Reported in ≥2% of Adult Treatment-Experienced Patients,b Study AI424-045
* None reported in this treatment arm.
a Includes events of possible, probable, certain, or unknown relationship to treatment regimen.
b Based on the regimen containing REYATAZ.
c Median time on therapy.
d As a fixed-dose combination.

48 weeksc
REYATAZ/ritonavir 300/100 mg
once daily + tenofovir + NRTI
(n=119)

48 weeksc
lopinavir/ritonavir 400/100 mg
twice dailyd + tenofovir + NRTI
(n=118)

Body as a Whole

Fever

2%

*

Digestive System

Jaundice/scleral icterus

9%

*

Diarrhea

3%

11%

Nausea

3%

2%

Nervous System

Depression

2%

<1%

Musculoskeletal System

Myalgia

4%

*

Laboratory Abnormalities in Treatment-Naive Patients

The percentages of adult treatment-naive patients treated with combination therapy including REYATAZ 300 mg with ritonavir 100 mg and REYATAZ 400 mg (without ritonavir) with Grade 3–4 laboratory abnormalities are presented in Tables 10 and 11, respectively.

Table 10: Grade 3�4 Laboratory Abnormalities Reported in ≥2% of Adult Treatment-Naive Patients,a Study AI424-138
a Based on the regimen containing REYATAZ.
b Median time on therapy.
c ULN = upper limit of normal.
d As a fixed-dose combination: 300 mg tenofovir, 200 mg emtricitabine once daily.

96 weeksb

REYATAZ 300 mg
with ritonavir 100 mg
(once daily) and tenofovir
with emtricitabined

96 weeksb

lopinavir 400 mg
with ritonavir 100 mg
(twice daily) and tenofovir
with emtricitabined

Variable

Limitc

(n=441)

(n=437)

Chemistry

High

SGOT/AST

≥5.1 × ULN

3%

1%

SGPT/ALT

≥5.1 × ULN

3%

2%

Total Bilirubin

≥2.6 × ULN

44%

<1%

Lipase

≥2.1 × ULN

2%

2%

Creatine Kinase

≥5.1 × ULN

8%

7%

Total Cholesterol

≥240 mg/dL

11%

25%

Hematology

Low

Neutrophils

<750 cells/mm3

5%

2%

Table 11: Grade 3–4 Laboratory Abnormalities Reported in ≥2% of Adult Treatment-Naive Patients,a Studies AI424-034, AI424-007, and AI424-008
* None reported in this treatment arm.
a Based on regimen(s) containing REYATAZ.
b Median time on therapy.
c Includes long-term follow-up.
d ULN = upper limit of normal.
e As a fixed-dose combination: 150 mg lamivudine, 300 mg zidovudine twice daily.

Study AI424-034

Studies AI424-007, -008

64 weeksb

REYATAZ
400 mg

once daily
+ lamivudine
+ zidovudinee

64 weeksb

efavirenz
600 mg
once daily
+ lamivudine
+ zidovudinee

120 weeksb,c

REYATAZ
400 mg
once daily
+ stavudine
+ lamivudine or
+ stavudine
+ didanosine

73 weeksb,c

nelfinavir
750 mg TID or
1250 mg BID
+ stavudine
+ lamivudine or
+ stavudine
+ didanosine

Variable

Limitd

(n=404)

(n=401)

(n=279)

(n=191)

Chemistry

High

SGOT/AST

≥5.1 × ULN

2%

2%

7%

5%

SGPT/ALT

≥5.1 × ULN

4%

3%

9%

7%

Total Bilirubin

≥2.6 × ULN

35%

<1%

47%

3%

Amylase

≥2.1 × ULN

*

*

14%

10%

Lipase

≥2.1 × ULN

<1%

1%

4%

5%

Creatine
Kinase

≥5.1 × ULN

6%

6%

11%

9%

Total Cholesterol

≥240 mg/dL

6%

24%

19%

48%

Triglycerides

≥751 mg/dL

<1%

3%

4%

2%

Hematology

Low

Hemoglobin

<8.0 g/dL

5%

3%

<1%

4%

Neutrophils

<750 cells/mm3

7%

9%

3%

7%

Change in Lipids from Baseline in Treatment-Naive Patients

For Study AI424-138 and Study AI424-034, changes from baseline in LDL-cholesterol, HDL-cholesterol, total cholesterol, and triglycerides are shown in Tables 12 and 13, respectively.

Table 12: Lipid Values, Mean Change from Baseline, Study AI424-138
a REYATAZ 300 mg with ritonavir 100 mg once daily with the fixed-dose combination: 300 mg tenofovir, 200 mg emtricitabine once daily.
b Values obtained after initiation of serum lipid-reducing agents were not included in these analyses. At baseline, serum lipid-reducing agents were used in 1% in the lopinavir/ritonavir treatment arm and 1% in the REYATAZ/ritonavir arm. Through Week 48, serum lipid-reducing agents were used in 8% in the lopinavir/ritonavir treatment arm and 2% in the REYATAZ/ritonavir arm. Through Week 96, serum lipid-reducing agents were used in 10% in the lopinavir/ritonavir treatment arm and 3% in the REYATAZ/ritonavir arm.
c Lopinavir 400 mg with ritonavir 100 mg twice daily with the fixed-dose combination 300 mg tenofovir, 200 mg emtricitabine once daily.
d The change from baseline is the mean of within-patient changes from baseline for patients with both baseline and Week 48 or Week 96 values and is not a simple difference of the baseline and Week 48 or Week 96 mean values, respectively.
e Number of patients with LDL-cholesterol measured.
f Fasting.

REYATAZ/ritonavira,b

lopinavir/ritonavirb,c

Baseline

Week 48

Week 96

Baseline

Week 48

Week 96

mg/dL

mg/dL

Changed

mg/dL

Changed

mg/dL

mg/dL

Changed

mg/dL

Changed

(n=428e)

(n=372e)

(n=372e)

(n=342e)

(n=342e)

(n=424e)

(n=335e)

(n=335e)

(n=291e)

(n=291e)

LDL-Cholesterolf

92

105

+14%

105

+14%

93

111

+19%

110

+17%

HDL-Cholesterolf

37

46

+29%

44

+21%

36

48

+37%

46

+29%

Total Cholesterolf

149

169

+13%

169

+13%

150

187

+25%

186

+25%

Triglyceridesf

126

145

+15%

140

+13%

129

194

+52%

184

+50%

Table 13: Lipid Values, Mean Change from Baseline, Study AI424-034
a REYATAZ 400 mg once daily with the fixed-dose combination: 150 mg lamivudine, 300 mg zidovudine twice daily.
b Values obtained after initiation of serum lipid-reducing agents were not included in these analyses. At baseline, serum lipid-reducing agents were used in 0% in the efavirenz treatment arm and <1% in the REYATAZ arm. Through Week 48, serum lipid-reducing agents were used in 3% in the efavirenz treatment arm and 1% in the REYATAZ arm.
c Efavirenz 600 mg once daily with the fixed-dose combination: 150 mg lamivudine, 300 mg zidovudine twice daily.
d The change from baseline is the mean of within-patient changes from baseline for patients with both baseline and Week 48 values and is not a simple difference of the baseline and Week 48 mean values.
e Number of patients with LDL-cholesterol measured.
f Fasting.

REYATAZa,b

efavirenzb,c

Baseline
mg/dL
(n=383e)

Week 48
mg/dL
(n=283e)

Week 48
Changed
(n=272e)

Baseline
mg/dL
(n=378e)

Week 48
mg/dL
(n=264e)

Week 48
Changed
(n=253e)

LDL-Cholesterolf

98

98

+1%

98

114

+18%

HDL-Cholesterol

39

43

+13%

38

46

+24%

Total Cholesterol

164

168

+2%

162

195

+21%

Triglyceridesf

138

124

−9%

129

168

+23%

Laboratory Abnormalities in Treatment-Experienced Patients

The percentages of adult treatment-experienced patients treated with combination therapy including REYATAZ/ritonavir with Grade 3–4 laboratory abnormalities are presented in Table 14.

Table 14: Grade 3–4 Laboratory Abnormalities Reported in ≥2% of Adult Treatment-Experienced Patients, Study AI424-045a
a Based on regimen(s) containing REYATAZ.
b Median time on therapy.
c ULN = upper limit of normal.
d As a fixed-dose combination.

48 weeksb

48 weeksb

REYATAZ/ritonavir
300/100 mg once daily +
tenofovir + NRTI

lopinavir/ritonavir
400/100 mg twice dailyd + tenofovir + NRTI

Variable

Limitc

(n=119)

(n=118)

Chemistry

High

SGOT/AST

≥5.1 × ULN

3%

3%

SGPT/ALT

≥5.1 × ULN

4%

3%

Total Bilirubin

≥2.6 × ULN

49%

<1%

Lipase

≥2.1 × ULN

5%

6%

Creatine Kinase

≥5.1 × ULN

8%

8%

Total Cholesterol

≥240 mg/dL

25%

26%

Triglycerides

≥751 mg/dL

8%

12%

Glucose

≥251 mg/dL

5%

<1%

Hematology

Low

Platelets

<50,000 cells/mm3

2%

3%

Neutrophils

<750 cells/mm3

7%

8%

Change in Lipids from Baseline in Treatment-Experienced Patients

For Study AI424-045, changes from baseline in LDL-cholesterol, HDL-cholesterol, total cholesterol, and triglycerides are shown in Table 15. The observed magnitude of dyslipidemia was less with REYATAZ/ritonavir than with lopinavir/ritonavir. However, the clinical impact of such findings has not been demonstrated.

Table 15: Lipid Values, Mean Change from Baseline, Study AI424-045
a REYATAZ 300 mg once daily + ritonavir + tenofovir + 1 NRTI.
b Values obtained after initiation of serum lipid-reducing agents were not included in these analyses. At baseline, serum lipid-reducing agents were used in 4% in the lopinavir/ritonavir treatment arm and 4% in the REYATAZ/ritonavir arm. Through Week 48, serum lipid-reducing agents were used in 19% in the lopinavir/ritonavir treatment arm and 8% in the REYATAZ/ritonavir arm.
c Lopinavir/ritonavir (400/100 mg) BID + tenofovir + 1 NRTI.
d The change from baseline is the mean of within-patient changes from baseline for patients with both baseline and Week 48 values and is not a simple difference of the baseline and Week 48 mean values.
e Number of patients with LDL-cholesterol measured.
f Fasting.

REYATAZ/ritonavira,b

lopinavir/ritonavirb,c

Baseline
mg/dL
(n=111e)

Week 48
mg/dL
(n=75e)

Week 48
Changed
(n=74e)

Baseline
mg/dL
(n=108e)

Week 48
mg/dL
(n=76e)

Week 48
Changed
(n=73e)

LDL-Cholesterolf

108

98

−10%

104

103

+1%

HDL-Cholesterol

40

39

−7%

39

41

+2%

Total Cholesterol

188

170

−8%

181

187

+6%

Triglyceridesf

215

161

−4%

196

224

+30%

Adverse Reactions in Pediatric Patients: REYATAZ Capsules

The safety and tolerability of REYATAZ Capsules with and without ritonavir have been established in pediatric patients at least 6 years of age from the open-label, multicenter clinical trial PACTG 1020A.

The safety profile of REYATAZ in pediatric patients (6 to less than 18 years of age) taking the capsule formulation was generally similar to that observed in clinical studies of REYATAZ in adults. The most common Grade 2–4 adverse events (≥5%, regardless of causality) reported in pediatric patients were cough (21%), fever (18%), jaundice/scleral icterus (15%), rash (14%), vomiting (12%), diarrhea (9%), headache (8%), peripheral edema (7%), extremity pain (6%), nasal congestion (6%), oropharyngeal pain (6%), wheezing (6%), and rhinorrhea (6%). Asymptomatic second-degree atrioventricular block was reported in <2% of patients. The most common Grade 3–4 laboratory abnormalities occurring in pediatric patients taking the capsule formulation were elevation of total bilirubin (≥3.2 mg/dL, 58%), neutropenia (9%), and hypoglycemia (4%). All other Grade 3–4 laboratory abnormalities occurred with a frequency of less than 3%.

Adverse Reactions in Pediatric Patients: REYATAZ Oral Powder

The data described below reflect exposure to REYATAZ oral powder in 155 subjects weighing at least 5 kg to less than 35 kg, including 134 patients exposed for 48 weeks. These data are from two pooled open-label, multi-center clinical trials in treatment-naive and treatment-experienced pediatric patients (AI424-397 [PRINCE I] and AI424-451 [PRINCE II]). Age ranged from 3 months to 10 years of age. In these studies 51% were female and 49% were male. All patients received ritonavir and 2 nucleoside reverse transcriptase inhibitors (NRTIs).

The safety profile of REYATAZ in pediatric patients taking REYATAZ oral powder was generally similar to that observed in clinical studies of REYATAZ in pediatric patients taking REYATAZ capsules. The most common Grade 3–4 laboratory abnormalities occurring in pediatric patients weighing 5 kg to less than 35 kg taking REYATAZ oral powder were increased amylase (33%), neutropenia (9%), increased SGPT/ALT (9%), elevation of total bilirubin (≥2.6 times ULN, 16%), and increased lipase (8%). All other Grade 3–4 laboratory abnormalities occurred with a frequency of less than 3%.

Adverse Reactions in Patients Co-Infected with Hepatitis B and/or Hepatitis C Virus

In study AI424-138, 60 patients treated with REYATAZ/ritonavir 300 mg/100 mg once daily, and 51 patients treated with lopinavir/ritonavir 400 mg/100 mg twice daily, each with fixed dose tenofovir-emtricitabine, were seropositive for hepatitis B and/or C at study entry. ALT levels >5 times ULN developed in 10% (6/60) of the REYATAZ/ritonavir-treated patients and 8% (4/50) of the lopinavir/ritonavir-treated patients. AST levels >5 times ULN developed in 10% (6/60) of the REYATAZ/ritonavir-treated patients and none (0/50) of the lopinavir/ritonavir-treated patients.

In study AI424-045, 20 patients treated with REYATAZ/ritonavir 300 mg/100 mg once daily, and 18 patients treated with lopinavir/ritonavir 400 mg/100 mg twice daily, were seropositive for hepatitis B and/or C at study entry. ALT levels >5 times ULN developed in 25% (5/20) of the REYATAZ/ritonavir-treated patients and 6% (1/18) of the lopinavir/ritonavir-treated patients. AST levels >5 times ULN developed in 10% (2/20) of the REYATAZ/ritonavir-treated patients and 6% (1/18) of the lopinavir/ritonavir-treated patients.

In studies AI424-008 and AI424-034, 74 patients treated with 400 mg of REYATAZ once daily, 58 who received efavirenz, and 12 who received nelfinavir were seropositive for hepatitis B and/or C at study entry. ALT levels >5 times ULN developed in 15% of the REYATAZ-treated patients, 14% of the efavirenz-treated patients, and 17% of the nelfinavir-treated patients. AST levels >5 times ULN developed in 9% of the REYATAZ-treated patients, 5% of the efavirenz-treated patients, and 17% of the nelfinavir-treated patients. Within REYATAZ and control regimens, no difference in frequency of bilirubin elevations was noted between seropositive and seronegative patients. [See WARNINGS AND PRECAUTIONS (5.3).]

6.2 Postmarketing Experience

The following events have been identified during postmarketing use of REYATAZ. Because these reactions are reported voluntarily from a population of unknown size, it is not always possible to reliably estimate their frequency or establish a causal relationship to drug exposure.

Body as a Whole: edema

Cardiovascular System: second-degree AV block, third-degree AV block, left bundle branch block, QTc prolongation [see WARNINGS AND PRECAUTIONS (5.1)]

Gastrointestinal System: pancreatitis

Hepatic System: hepatic function abnormalities

Hepatobiliary Disorders: cholelithiasis [see WARNINGS AND PRECAUTIONS (5.5)], cholecystitis, cholestasis

Metabolic System and Nutrition Disorders: diabetes mellitus, hyperglycemia [see WARNINGS AND PRECAUTIONS (5.8)]

Musculoskeletal System: arthralgia

Renal System: nephrolithiasis [see WARNINGS AND PRECAUTIONS (5.6)], interstitial nephritis

Skin and Appendages: alopecia, maculopapular rash [see CONTRAINDICATIONS (4) and WARNINGS AND PRECAUTIONS (5.2)], pruritus, angioedema

7 DRUG INTERACTIONS

7.1 Potential for REYATAZ to Affect Other Drugs

Atazanavir is an inhibitor of CYP3A and UGT1A1. Coadministration of REYATAZ and drugs primarily metabolized by CYP3A or UGT1A1 may result in increased plasma concentrations of the other drug that could increase or prolong its therapeutic and adverse effects.

Atazanavir is a weak inhibitor of CYP2C8. Use of REYATAZ without ritonavir is not recommended when coadministered with drugs highly dependent on CYP2C8 with narrow therapeutic indices (eg, paclitaxel, repaglinide). When REYATAZ with ritonavir is coadministered with substrates of CYP2C8, clinically significant interactions are not expected [see CLINICAL PHARMACOLOGY, TABLE 22 (12.3)].

The magnitude of CYP3A-mediated drug interactions on coadministered drug may change when REYATAZ is coadministered with ritonavir. See the complete prescribing information for ritonavir for information on drug interactions with ritonavir.

7.2 Potential for Other Drugs to Affect REYATAZ

Atazanavir is a CYP3A4 substrate; therefore, drugs that induce CYP3A4 may decrease atazanavir plasma concentrations and reduce REYATAZ’s therapeutic effect.

Atazanavir solubility decreases as pH increases. Reduced plasma concentrations of atazanavir are expected if proton-pump inhibitors, antacids, buffered medications, or H2-receptor antagonists are administered with REYATAZ [see DOSAGE AND ADMINISTRATION (2.2, 2.3, 2.4, and 2.5)].

7.3 Established and Other Potentially Significant Drug Interactions

Table 16 provides dosing recommendations in adults as a result of drug interactions with REYATAZ. These recommendations are based on either drug interaction studies or predicted interactions due to the expected magnitude of interaction and potential for serious events or loss of efficacy.

Table 16: Established and Other Potentially Significant Drug Interactions: Alteration in Dose or Regimen May Be Recommended Based on Drug Interaction Studiesa or Predicted Interactions (Information in the table applies to REYATAZ with or without ritonavir, unless otherwise indicated)
Concomitant Drug Class:
Specific Drugs Effect on Concentration of Atazanavir or Concomitant Drug Clinical Comment
a For magnitude of interactions see CLINICAL PHARMACOLOGY, TABLES 21 AND 22 (12.3).
b See CONTRAINDICATIONS (4), TABLE 6 for orally administered midazolam.
c In combination with atazanavir 300 mg and ritonavir 100 mg once daily.
d In combination with atazanavir 400 mg once daily.

HIV Antiviral Agents

Nucleoside Reverse Transcriptase Inhibitors (NRTIs):
didanosine buffered formulations
enteric-coated (EC) capsules

↓ atazanavir
↓ didanosine

Coadministration of REYATAZ with didanosine buffered tablets resulted in a marked decrease in atazanavir exposure. It is recommended that REYATAZ be given (with food) 2 h before or 1 h after didanosine buffered formulations. Simultaneous administration of didanosine EC and REYATAZ with food results in a decrease in didanosine exposure. Thus, REYATAZ and didanosine EC should be administered at different times.

Nucleotide Reverse Transcriptase Inhibitors:
tenofovir disoproxil fumarate

↓ atazanavir
↑ tenofovir

Tenofovir may decrease the AUC and Cmin of atazanavir. When coadministered with tenofovir in adults, it is recommended that REYATAZ 300 mg be given with ritonavir 100 mg and tenofovir 300 mg (all as a single daily dose with food). REYATAZ increases tenofovir concentrations. The mechanism of this interaction is unknown. Higher tenofovir concentrations could potentiate tenofovir-associated adverse reactions, including renal disorders. Patients receiving REYATAZ and tenofovir should be monitored for tenofovir-associated adverse reactions. For pregnant women taking REYATAZ with ritonavir and tenofovir, see DOSAGE AND ADMINISTRATION (2.5).

Non-nucleoside Reverse Transcriptase Inhibitors (NNRTIs):
efavirenz

↓ atazanavir

Efavirenz decreases atazanavir exposure.

In treatment-naive adult patients:

If REYATAZ is combined with efavirenz, REYATAZ 400 mg (two 200-mg capsules) should be administered with ritonavir 100 mg simultaneously once daily with food, and efavirenz 600 mg should be administered once daily on an empty stomach, preferably at bedtime.

In treatment-experienced adult patients:

Coadministration of REYATAZ with efavirenz in treatment-experienced patients is not recommended due to decreased atazanavir exposure.

Protease Inhibitors:
saquinavir (soft gelatin capsules)

↑ saquinavir

Appropriate dosing recommendations for this combination, with or without ritonavir, with respect to efficacy and safety have not been established. In a clinical study, saquinavir 1200 mg coadministered with REYATAZ 400 mg and tenofovir 300 mg (all given once daily) plus nucleoside analogue reverse transcriptase inhibitors did not provide adequate efficacy [see CLINICAL STUDIES (14.2)].

ritonavir

↑ atazanavir

If REYATAZ is coadministered with ritonavir, it is recommended that REYATAZ 300 mg once daily be given with ritonavir 100 mg once daily with food in adults. See the complete prescribing information for ritonavir for information on drug interactions with ritonavir.

others

↑ other protease inhibitor

Although not studied, the coadministration of REYATAZ/ritonavir and an additional protease inhibitor would be expected to increase exposure to the other protease inhibitor. Such coadministration is not recommended.

HCV Antiviral Agents

Protease Inhibitors:
boceprevir

↓ atazanavir
↓ ritonavir

Concomitant administration of boceprevir and atazanavir/ritonavir resulted in reduced steady-state exposures to atazanavir and ritonavir. Coadministration of REYATAZ/ritonavir and boceprevir is not recommended.

Other Agents

Antacids and buffered medications

↓ atazanavir

Reduced plasma concentrations of atazanavir are expected if antacids, including buffered medications, are administered with REYATAZ. REYATAZ should be administered 2 hours before or 1 hour after these medications.

Antiarrhythmics:
amiodarone, bepridil, lidocaine (systemic), quinidine

↑ amiodarone, bepridil, lidocaine (systemic), quinidine

Coadministration with REYATAZ has the potential to produce serious and/or life-threatening adverse events and has not been studied. Caution is warranted and therapeutic concentration monitoring of these drugs is recommended if they are used concomitantly with REYATAZ.

Anticoagulants:
warfarin

↑ warfarin

Coadministration with REYATAZ has the potential to produce serious and/or life-threatening bleeding and has not been studied. It is recommended that International Normalized Ratio (INR) be monitored.

Antidepressants:
tricyclic antidepressants

↑ tricyclic antidepressants

Coadministration with REYATAZ has the potential to produce serious and/or life-threatening adverse events and has not been studied. Concentration monitoring of these drugs is recommended if they are used concomitantly with REYATAZ.

trazodone

↑ trazodone

Concomitant use of trazodone and REYATAZ with or without ritonavir may increase plasma concentrations of trazodone. Nausea, dizziness, hypotension, and syncope have been observed following coadministration of trazodone and ritonavir. If trazodone is used with a CYP3A4 inhibitor such as REYATAZ, the combination should be used with caution and a lower dose of trazodone should be considered.

Antiepileptics:
carbamazepine

↓ atazanavir
↑ carbamazepine

Plasma concentrations of atazanavir may be decreased when carbamazepine is administered with REYATAZ without ritonavir. Coadministration of carbamazepine and REYATAZ without ritonavir is not recommended. Ritonavir may increase plasma levels of carbamazepine. If patients beginning treatment with REYATAZ/ritonavir have been titrated to a stable dose of carbamazepine, a dose reduction for carbamazepine may be necessary.

phenytoin, phenobarbital

↓ atazanavir
↓ phenytoin
↓ phenobarbital

Plasma concentrations of atazanavir may be decreased when phenytoin or phenobarbital is administered with REYATAZ without ritonavir. Coadministration of phenytoin or phenobarbital and REYATAZ without ritonavir is not recommended. Ritonavir may decrease plasma levels of phenytoin and phenobarbital. When REYATAZ with ritonavir is coadministered with either phenytoin or phenobarbital, a dose adjustment of phenytoin or phenobarbital may be required.

lamotrigine

↓ lamotrigine

Coadministration of lamotrigine and REYATAZ with ritonavir may decrease lamotrigine plasma concentrations. Dose adjustment of lamotrigine may be required when coadministered with REYATAZ and ritonavir. Coadministration of lamotrigine and REYATAZ without ritonavir is not expected to decrease lamotrigine plasma concentrations. No dose adjustment of lamotrigine is required when coadministered with REYATAZ without ritonavir.

Antifungals:
ketoconazole, itraconazole

REYATAZ/ritonavir:
↑ ketoconazole
↑ itraconazole

Coadministration of ketoconazole has only been studied with REYATAZ without ritonavir (negligible increase in atazanavir AUC and Cmax). Due to the effect of ritonavir on ketoconazole, high doses of ketoconazole and itraconazole (>200 mg/day) should be used cautiously with REYATAZ/ritonavir.

voriconazole

REYATAZ/ritonavir in subjects with a functional CYP2C19 allele:
↓ voriconazole
↓ atazanavir
REYATAZ/ritonavir in subjects without a functional CYP2C19 allele:
↑ voriconazole
↓ atazanavir

The use of voriconazole in patients receiving REYATAZ/ritonavir is not recommended unless an assessment of the benefit/risk to the patient justifies the use of voriconazole. Patients should be carefully monitored for voriconazole-associated adverse reactions and loss of either voriconazole or atazanavir efficacy during the coadministration of voriconazole and REYATAZ/ritonavir. Coadministration of voriconazole with REYATAZ (without ritonavir) may affect atazanavir concentrations; however, no data are available.

Antigout:
colchicine

↑ colchicine

The coadministration of REYATAZ with colchicine in patients with renal or hepatic impairment is not recommended.

Recommended adult dosage of colchicine when administered with REYATAZ:

Treatment of gout flares:

0.6 mg (1 tablet) for 1 dose, followed by 0.3 mg (half tablet) 1 hour later. Not to be repeated before 3 days.

Prophylaxis of gout flares:

If the original regimen was 0.6 mg twice a day, the regimen should be adjusted to 0.3 mg once a day.

If the original regimen was 0.6 mg once a day, the regimen should be adjusted to 0.3 mg once every other day.

Treatment of familial Mediterranean fever (FMF):

Maximum daily dose of 0.6 mg (may be given as 0.3 mg twice a day).

Antimycobacterials:
rifabutin

↑ rifabutin

A rifabutin dose reduction of up to 75% (eg, 150 mg every other day or 3 times per week) is recommended. Increased monitoring for rifabutin-associated adverse reactions including neutropenia is warranted.

Antipsychotics:
quetiapine and lurasidone

↑ quetiapine

Init.iation of REYATAZ with ritonavir in patients taking quetiapine:
Consider alternative antiretroviral therapy to avoid increases in quetiapine exposures. If coadministration is necessary, reduce the quetiapine dose to 1/6 of the current dose and monitor for quetiapine-associated adverse reactions. Refer to the quetiapine prescribing information for recommendations on adverse reaction monitoring.
Initiation of quetiapine in patients taking REYATAZ with ritonavir:
Refer to the quetiapine prescribing information for initial dosing and titration of quetiapine.

REYATAZ

↑ lurasidone

REYATAZ without ritonavir

If coadministration is necessary, reduce the lurasidone dose. Refer to the lurasidone prescribing information for concomitant use with moderate CYP3A4 inhibitors

REYATAZ/ritonavir

↑ lurasidone

REYATAZ/ritonavir

Use of lurasidone is contraindicated.

Benzodiazepines:
parenterally administered midazolamb

↑ midazolam

Concomitant use of parenteral midazolam with REYATAZ may increase plasma concentrations of midazolam. Coadministration should be done in a setting which ensures close clinical monitoring and appropriate medical management in case of respiratory depression and/or prolonged sedation. Dosage reduction for midazolam should be considered, especially if more than a single dose of midazolam is administered. Coadministration of oral midazolam with REYATAZ is CONTRAINDICATED.

Calcium channel blockers:
diltiazem

↑ diltiazem and desacetyl-diltiazem

Caution is warranted. A dose reduction of diltiazem by 50% should be considered. ECG monitoring is recommended. Coadministration of REYATAZ/ritonavir with diltiazem has not been studied.

felodipine, nifedipine, nicardipine, and verapamil

↑ calcium channel blocker

Caution is warranted. Dose titration of the calcium channel blocker should be considered. ECG monitoring is recommended.

Endothelin receptor antagonists:
bosentan

↓ atazanavir
↑ bosentan

Plasma concentrations of atazanavir may be decreased when bosentan is administered with REYATAZ without ritonavir. Coadministration of bosentan and REYATAZ without ritonavir is not recommended.

Coadministration of bosentan in adult patients on REYATAZ/ritonavir:

For patients who have been receiving REYATAZ/ritonavir for at least 10 days, start bosentan at 62.5 mg once daily or every other day based on individual tolerability.

Coadministration of REYATAZ/ritonavir in adult patients on bosentan:

Discontinue bosentan at least 36 hours before starting REYATAZ/ritonavir. At least 10 days after starting REYATAZ/ritonavir, resume bosentan at 62.5 mg once daily or every other day based on individual tolerability.

HMG-CoA reductase inhibitors:
atorvastatin, rosuvastatin

↑ atorvastatin
↑ rosuvastatin

Titrate atorvastatin dose carefully and use the lowest necessary dose. Rosuvastatin dose should not exceed 10 mg/day. The risk of myopathy, including rhabdomyolysis, may be increased when HIV protease inhibitors, including REYATAZ, are used in combination with these drugs.

H2‑Receptor antagonists

↓ atazanavir

Plasma concentrations of atazanavir were substantially decreased when REYATAZ 400 mg once daily was administered simultaneously with famotidine 40 mg twice daily in adults, which may result in loss of therapeutic effect and development of resistance.

In treatment-naive adult patients:

REYATAZ 300 mg with ritonavir 100 mg once daily with food should be administered simultaneously with, and/or at least 10 hours after, a dose of the H2-receptor antagonist (H2RA). An H2RA dose comparable to famotidine 20 mg once daily up to a dose comparable to famotidine 40 mg twice daily can be used with REYATAZ 300 mg with ritonavir 100 mg in treatment-naive patients.

OR

For patients unable to tolerate ritonavir, REYATAZ 400 mg once daily with food should be administered at least 2 hours before and at least 10 hours after a dose of the H2RA. No single dose of the H2RA should exceed a dose comparable to famotidine 20 mg, and the total daily dose should not exceed a dose comparable to famotidine 40 mg. The use of REYATAZ without ritonavir in pregnant women is not recommended.

In treatment-experienced adult patients:

Whenever an H2RA is given to a patient receiving REYATAZ with ritonavir, the H2RA dose should not exceed a dose comparable to famotidine 20 mg twice daily, and the REYATAZ and ritonavir doses should be administered simultaneously with, and/or at least 10 hours after, the dose of the H2RA.

•
REYATAZ 300 mg with ritonavir 100 mg once daily (all as a single dose with food) if taken with an H2RA.
•
REYATAZ 400 mg with ritonavir 100 mg once daily (all as a single dose with food) if taken with both tenofovir and an H2RA.
•
REYATAZ 400 mg with ritonavir 100 mg once daily (all as a single dose with food) if taken with either tenofovir or an H2RA for pregnant women during the second and third trimester. REYATAZ is not recommended for pregnant women during the second and third trimester taking REYATAZ with both tenofovir and an H2RA.

Hormonal contraceptives:
ethinyl estradiol and norgestimate or norethindrone

↓ ethinyl estradiol
↑ norgestimatec

↑ ethinyl estradiol
↑ norethindroned

Use with caution if coadministration of REYATAZ or REYATAZ/ritonavir with oral contraceptives is considered. If an oral contraceptive is administered with REYATAZ plus ritonavir, it is recommended that the oral contraceptive contain at least 35 mcg of ethinyl estradiol. If REYATAZ is administered without ritonavir, the oral contraceptive should contain no more than 30 mcg of ethinyl estradiol.

Potential safety risks include substantial increases in progesterone exposure. The long-term effects of increases in concentration of the progestational agent are unknown and could increase the risk of insulin resistance, dyslipidemia, and acne.

Coadministration of REYATAZ or REYATAZ/ritonavir with other hormonal contraceptives (eg, contraceptive patch, contraceptive vaginal ring, or injectable contraceptives) or oral contraceptives containing progestogens other than norethindrone or norgestimate, or less than 25 mcg of ethinyl estradiol, has not been studied; therefore, alternative methods of contraception are recommended.

Immunosuppressants:
cyclosporine, sirolimus, tacrolimus

↑ immunosuppressants

Therapeutic concentration monitoring is recommended for these immunosuppressants when coadministered with REYATAZ.

Inhaled beta agonist:
salmeterol

↑ salmeterol

Coadministration of salmeterol with REYATAZ is not recommended. Concomitant use of salmeterol and REYATAZ may result in increased risk of cardiovascular adverse reactions associated with salmeterol, including QT prolongation, palpitations, and sinus tachycardia.

Inhaled/nasal steroid:
fluticasone

REYATAZ
↑ fluticasone

Concomitant use of fluticasone propionate and REYATAZ (without ritonavir) may increase plasma concentrations of fluticasone propionate. Use with caution. Consider alternatives to fluticasone propionate, particularly for long-term use.

REYATAZ/ritonavir
↑ fluticasone

Concomitant use of fluticasone propionate and REYATAZ/ritonavir may increase plasma concentrations of fluticasone propionate, resulting in significantly reduced serum cortisol concentrations. Systemic corticosteroid effects, including Cushing’s syndrome and adrenal suppression, have been reported during postmarketing use in patients receiving ritonavir and inhaled or intranasally administered fluticasone propionate. Coadministration of fluticasone propionate and REYATAZ/ritonavir is not recommended unless the potential benefit to the patient outweighs the risk of systemic corticosteroid side effects [see WARNINGS AND PRECAUTIONS (5.1)].

Macrolide antibiotics:
clarithromycin

↑ clarithromycin
↓ 14-OH clarithromycin
↑ atazanavir

Increased concentrations of clarithromycin may cause QTc prolongations; therefore, a dose reduction of clarithromycin by 50% should be considered when it is coadministered with REYATAZ. In addition, concentrations of the active metabolite 14-OH clarithromycin are significantly reduced; consider alternative therapy for indications other than infections due to Mycobacterium avium complex. Coadministration of REYATAZ/ritonavir with clarithromycin has not been studied.

Opioids:
Buprenorphine

↑ buprenorphine
↑ norbuprenorphine

Coadministration of buprenorphine and REYATAZ with or without ritonavir increases the plasma concentration of buprenorphine and norbuprenorphine. Coadministration of REYATAZ plus ritonavir with buprenorphine warrants clinical monitoring for sedation and cognitive effects. A dose reduction of buprenorphine may be considered. Coadministration of buprenorphine and REYATAZ with ritonavir is not expected to decrease atazanavir plasma concentrations. Coadministration of buprenorphine and REYATAZ without ritonavir may decrease atazanavir plasma concentrations. The coadministration of REYATAZ and buprenorphine without ritonavir is not recommended.

PDE5 inhibitors:
sildenafil, tadalafil, vardenafil

↑ sildenafil
↑ tadalafil
↑ vardenafil

Coadministration with REYATAZ has not been studied but may result in an increase in PDE5 inhibitor-associated adverse reactions, including hypotension, syncope, visual disturbances, and priapism.

Use of PDE5 inhibitors for pulmonary arterial hypertension (PAH):

Use of REVATIO ® (sildenafil) for the treatment of pulmonary hypertension (PAH) is contraindicated with REYATAZ [see CONTRAINDICATIONS (4)].
The following dose adjustments are recommended for the use of ADCIRCA ® (tadalafil) with REYATAZ:
Coadministration of ADCIRCA ® in patients on REYATAZ (with or without ritonavir):

•
For patients receiving REYATAZ (with or without ritonavir) for at least one week, start ADCIRCA ® at 20 mg once daily. Increase to 40 mg once daily based on individual tolerability.

Coadministration of REYATAZ (with or without ritonavir) in patients on ADCIRCA ®:

•
Avoid the use of ADCIRCA ® when starting REYATAZ (with or without ritonavir). Stop ADCIRCA ® at least 24 hours before starting REYATAZ (with or without ritonavir). At least one week after starting REYATAZ (with or without ritonavir), resume ADCIRCA ® at 20 mg once daily. Increase to 40 mg once daily based on individual tolerability.

Use of PDE5 inhibitors for erectile dysfunction:

Use VIAGRA ® (sildenafil) with caution at reduced doses of 25 mg every 48 hours with increased monitoring for adverse events.
Use CIALIS ® (tadalafil) with caution at reduced doses of 10 mg every 72 hours with increased monitoring for adverse events.
REYATAZ/ritonavir: Use vardenafil with caution at reduced doses of no more than 2.5 mg every 72 hours with increased monitoring for adverse reactions.
REYATAZ: Use vardenafil with caution at reduced doses of no more than 2.5 mg every 24 hours with increased monitoring for adverse reactions.

Proton-pump inhibitors:
omeprazole

↓ atazanavir

Plasma concentrations of atazanavir were substantially decreased when REYATAZ 400 mg or REYATAZ 300 mg/ritonavir 100 mg once daily was administered with omeprazole 40 mg once daily in adults, which may result in loss of therapeutic effect and development of resistance.

In treatment-naive adult patients:

The proton-pump inhibitor (PPI) dose should not exceed a dose comparable to omeprazole 20 mg and must be taken approximately 12 hours prior to the REYATAZ 300 mg with ritonavir 100 mg dose.

In treatment-experienced adult patients:

The use of PPIs in treatment-experienced patients receiving REYATAZ is not recommended.

7.4 Drugs with No Observed Interactions with REYATAZ

No clinically significant drug interactions were observed when REYATAZ was coadministered with methadone, fluconazole, acetaminophen, atenolol, or the nucleoside reverse transcriptase inhibitors lamivudine or zidovudine [see CLINICAL PHARMACOLOGY, TABLES 21 AND 22 (12.3)].

8 USE IN SPECIFIC POPULATIONS

8.1 Pregnancy

Pregnancy Exposure Registry

There is a pregnancy exposure registry that monitors pregnancy outcomes in women exposed to REYATAZ during pregnancy. Healthcare providers are encouraged to register patients by calling the Antiretroviral Pregnancy Registry (APR) at 1-800-258-4263.

Risk Summary

Atazanavir has been evaluated in a limited number of women during pregnancy. Available human and animal data suggest that atazanavir does not increase the risk of major birth defects overall compared to the background rate [see DATA]. In the U.S. general population, the estimated background risk of major birth defects and miscarriage in clinically recognized pregnancies is 2-4% and 15-20%, respectively. No treatment-related malformations were observed in rats and rabbits, for which the atazanavir exposures were 0.7-1.2 times of those at the human clinical dose (300 mg/day atazanavir boosted with 100 mg/day ritonavir). When atazanavir was administered to rats during pregnancy and throughout lactation, reversible neonatal growth retardation was observed [see DATA].

Clinical Considerations

Dose Adjustments during Pregnancy and the Postpartum Period

•
REYATAZ must be administered with ritonavir in pregnant women.
•
For pregnant patients, no dosage adjustment is required for REYATAZ with the following exceptions:

•
For treatment-experienced pregnant women during the second or third trimester, when REYATAZ is coadministered with either an H 2-receptor antagonist or tenofovir, REYATAZ 400 mg with ritonavir 100 mg once daily is recommended. There are insufficient data to recommend a REYATAZ dose for use with both an H 2-receptor antagonist and tenofovir in treatment-experienced pregnant women.

•
No dosage adjustment is required for postpartum patients. However, patients should be closely monitored for adverse events because atazanavir exposures could be higher during the first 2 months after delivery [see DOSAGE AND ADMINISTRATION (2.5) and CLINICAL PHARMACOLOGY (12.3)].

Maternal Adverse Reactions

Cases of lactic acidosis syndrome, sometimes fatal, and symptomatic hyperlactatemia have occurred in pregnant women using REYATAZ in combination with nucleoside analogues, which are associated with an increased risk of lactic acidosis syndrome.

Hyperbilirubinemia occurs frequently in patients who take REYATAZ [see WARNINGS AND PRECAUTIONS (5.3)], including pregnant women [see DATA].

Advise pregnant women of the potential risks of lactic acidosis syndrome and hyperbilirubinemia.

Fetal/Neonatal Adverse Reactions

All infants, including neonates exposed to REYATAZ in utero, should be monitored for the development of severe hyperbilirubinemia during the first few days of life [see DATA].

Data

Human Data

In clinical trial AI424-182, REYATAZ/ritonavir (300/100 mg or 400/100 mg) in combination with zidovudine/lamivudine was administered to 41 HIV-infected pregnant women during the second or third trimester. Among the 39 women who completed the study, 38 women achieved an HIV RNA less than 50 copies/mL at time of delivery. Six of 20 (30%) women on REYATAZ/ritonavir 300/100 mg and 13 of 21 (62%) women on REYATAZ/ritonavir 400/100 mg experienced hyperbilirubinemia (total bilirubin greater than or equal to 2.6 times ULN). There were no cases of lactic acidosis observed in clinical trial AI424-182.

Atazanavir drug concentrations in fetal umbilical cord blood were approximately 12% to 19% of maternal concentrations. Among the 40 infants born to 40 HIV-infected pregnant women, all had test results that were negative for HIV-1 DNA at the time of delivery and/or during the first 6 months postpartum. All 40 infants received antiretroviral prophylactic treatment containing zidovudine. No evidence of severe hyperbilirubinemia (total bilirubin levels greater than 20 mg/dL) or acute or chronic bilirubin encephalopathy was observed among neonates in this study. However, 10/36 (28%) infants (6 greater than or equal to 38 weeks gestation and 4 less than 38 weeks gestation) had bilirubin levels of 4 mg/dL or greater within the first day of life.

Lack of ethnic diversity was a study limitation. In the study population, 33/40 (83%) infants were Black/African American, who have a lower incidence of neonatal hyperbilirubinemia than Caucasians and Asians. In addition, women with Rh incompatibility were excluded, as well as women who had a previous infant who developed hemolytic disease and/or had neonatal pathologic jaundice (requiring phototherapy).

Additionally, of the 38 infants who had glucose samples collected in the first day of life, 3 had adequately collected serum glucose samples with values of less than 40 mg/dL that could not be attributed to maternal glucose intolerance, difficult delivery, or sepsis.

Based on prospective reports from the APR of approximately 1600 live births following exposure to atazanavir-containing regimens (including 1037 live births in infants exposed in the first trimester and 569 exposed in second/third trimesters), there was no difference between atazanavir and overall birth defects compared with the background birth defect rate. In the U.S. general population, the estimated background risk of major birth defects in clinically recognized pregnancies is 2-4%.

Animal Data

In animal reproduction studies, there was no evidence of mortality or teratogenicity in offspring born to animals at systemic drug exposure levels (AUC) 0.7 (in rabbits) to 1.2 (in rats) times those observed at the human clinical dose (300 mg/day atazanavir boosted with 100 mg/day ritonavir). In pre- and postnatal development studies in the rat, atazanavir caused neonatal growth retardation during lactation that reversed after weaning. Maternal drug exposure at this dose was 1.3 times the human exposure at the recommended clinical exposure. Minimal maternal toxicity occurred at this exposure level.

8.2 Lactation

Risk Summary

The Centers for Disease Control and Prevention recommend that HIV-1 infected mothers not breastfeed their infants to avoid risking postnatal transmission of HIV-1. Atazanavir has been detected in human milk. No data are available regarding atazanavir effects on milk production. Atazanavir was present in the milk of lactating rats and was associated with neonatal growth retardation that reversed after weaning.

Because of both the potential for HIV-1 transmission and the potential for serious adverse reactions in breastfed infants, advise women not to breastfeed.

8.4 Pediatric Use

REYATAZ is indicated in combination with other antiretroviral agents for the treatment of HIV-1 infection in pediatric patients 3 months of age and older weighing at least 5 kg. REYATAZ is not recommended for use in pediatric patients below the age of 3 months due to the risk of kernicterus [see INDICATIONS AND USAGE (1)]. All REYATAZ contraindications, warnings, and precautions apply to pediatric patients [see CONTRAINDICATIONS (4) and WARNINGS AND PRECAUTIONS (5)].

The safety, pharmacokinetic profile, and virologic response of REYATAZ in pediatric patients at least 3 months of age and older weighing at least 5 kg were established in three open-label, multicenter clinical trials: PACTG 1020A, AI424-451, and AI424-397 [see CLINICAL PHARMACOLOGY (12.3) and CLINICAL STUDIES (14.3)]. The safety profile in pediatric patients was generally similar to that observed in adults [see ADVERSE REACTIONS (6.1)]. See DOSAGE AND ADMINISTRATION (2.3, 2.4) for dosing recommendations for the use of REYATAZ capsules and REYATAZ oral powder in pediatric patients.

8.5 Geriatric Use

Clinical studies of REYATAZ did not include sufficient numbers of patients aged 65 and over to determine whether they respond differently from younger patients. Based on a comparison of mean single-dose pharmacokinetic values for Cmax and AUC, a dose adjustment based upon age is not recommended. In general, appropriate caution should be exercised in the administration and monitoring of REYATAZ in elderly patients reflecting the greater frequency of decreased hepatic, renal, or cardiac function, and of concomitant disease or other drug therapy.

8.6 Age/Gender

A study of the pharmacokinetics of atazanavir was performed in young (n=29; 18-40 years) and elderly (n=30; ≥65 years) healthy subjects. There were no clinically significant pharmacokinetic differences observed due to age or gender.

8.7 Impaired Renal Function

REYATAZ is not recommended for use in HIV-treatment-experienced patients with end stage renal disease managed with hemodialysis [see DOSAGE AND ADMINISTRATION (2.6) and CLINICAL PHARMACOLOGY (12.3)].

8.8 Impaired Hepatic Function

REYATAZ is not recommended for use in patients with severe hepatic impairment. REYATAZ/ritonavir is not recommended in patients with any degree of hepatic impairment [see DOSAGE AND ADMINISTRATION (2.7) and CLINICAL PHARMACOLOGY (12.3)].

10 OVERDOSAGE

Human experience of acute overdose with REYATAZ is limited. Single doses up to 1200 mg (three times the 400 mg maximum recommended dose) have been taken by healthy volunteers without symptomatic untoward effects. A single self-administered overdose of 29.2 g of REYATAZ in an HIV-infected patient (73 times the 400-mg recommended dose) was associated with asymptomatic bifascicular block and PR interval prolongation. These events resolved spontaneously. At REYATAZ doses resulting in high atazanavir exposures, jaundice due to indirect (unconjugated) hyperbilirubinemia (without associated liver function test changes) or PR interval prolongation may be observed [see WARNINGS AND PRECAUTIONS (5.1, 5.3) and CLINICAL PHARMACOLOGY (12.2)].

Treatment of overdosage with REYATAZ should consist of general supportive measures, including monitoring of vital signs and ECG, and observations of the patient’s clinical status. If indicated, elimination of unabsorbed atazanavir should be achieved by emesis or gastric lavage. Administration of activated charcoal may also be used to aid removal of unabsorbed drug. There is no specific antidote for overdose with REYATAZ. Since atazanavir is extensively metabolized by the liver and is highly protein bound, dialysis is unlikely to be beneficial in significant removal of this medicine.

11 DESCRIPTION

The active ingredient in REYATAZ capsules and oral powder is atazanavir sulfate, which is an HIV-1 protease inhibitor.

The chemical name for atazanavir sulfate is (3S,8S,9S,12S)-3,12-Bis(1,1-dimethylethyl)-8-hydroxy-4,11-dioxo-9-(phenylmethyl)-6-[[4-(2-pyridinyl)phenyl]methyl]-2,5,6,10,13-pentaazatetradecanedioic acid dimethyl ester, sulfate (1:1). Its molecular formula is C38H52N6O7•H2SO4, which corresponds to a molecular weight of 802.9 (sulfuric acid salt). The free base molecular weight is 704.9. Atazanavir sulfate has the following structural formula:

[Reyataz Chemical Structure]

Atazanavir sulfate is a white to pale-yellow crystalline powder. It is slightly soluble in water

(4-5 mg/mL, free base equivalent) with the pH of a saturated solution in water being about 1.9 at 24 ± 3°C.

REYATAZ Capsules are available for oral administration in strengths of 150 mg, 200 mg, or 300 mg of atazanavir, which are equivalent to 170.8 mg, 227.8 mg, or 341.69 mg of atazanavir sulfate, respectively. The capsules also contain the following inactive ingredients: crospovidone, lactose monohydrate, and magnesium stearate. The capsule shells contain the following inactive ingredients: gelatin, FD&C Blue No. 2, titanium dioxide, black iron oxide, red iron oxide, and yellow iron oxide. The capsules are printed with ink containing shellac, titanium dioxide, FD&C Blue No. 2, isopropyl alcohol, ammonium hydroxide, propylene glycol, n-butyl alcohol, simethicone, and dehydrated alcohol.

REYATAZ oral powder comes in a packet containing 50 mg of atazanavir equivalent to 56.9 mg of atazanavir sulfate in 1.5 g of powder. The powder is off-white to pale yellow and contains the following inactive ingredients: aspartame, sucrose, and orange-vanilla flavor.

12 CLINICAL PHARMACOLOGY

12.1 Mechanism of Action

Atazanavir is an HIV-1 antiretroviral drug [see MICROBIOLOGY (12.4)].

12.2 Pharmacodynamics

Cardiac Electrophysiology

Concentration- and dose-dependent prolongation of the PR interval in the electrocardiogram has been observed in healthy volunteers receiving atazanavir. In a placebo-controlled study (AI424-076), the mean (±SD) maximum change in PR interval from the predose value was 24 (±15) msec following oral dosing with 400 mg of atazanavir (n=65) compared to 13 (±11) msec following dosing with placebo (n=67). The PR interval prolongations in this study were asymptomatic. There is limited information on the potential for a pharmacodynamic interaction in humans between atazanavir and other drugs that prolong the PR interval of the electrocardiogram [see WARNINGS AND PRECAUTIONS (5.1)].

Electrocardiographic effects of atazanavir were determined in a clinical pharmacology study of 72 healthy subjects. Oral doses of 400 mg (maximum recommended dosage) and 800 mg (twice the maximum recommended dosage) were compared with placebo; there was no concentration-dependent effect of atazanavir on the QTc interval (using Fridericia’s correction). In 1793 HIV-infected patients receiving antiretroviral regimens, QTc prolongation was comparable in the atazanavir and comparator regimens. No atazanavir-treated healthy subject or HIV-infected patient in clinical trials had a QTc interval >500 msec [see WARNINGS AND PRECAUTIONS (5.1)].

12.3 Pharmacokinetics

The pharmacokinetics of atazanavir were evaluated in healthy adult volunteers and in HIV-infected patients after administration of REYATAZ 400 mg once daily and after administration of REYATAZ 300 mg with ritonavir 100 mg once daily (see Table 17).

Table 17: Steady-State Pharmacokinetics of Atazanavir in Healthy Subjects or HIV-Infected Patients in the Fed State
a n=26.
b n=12.

400 mg once daily

300 mg with ritonavir
100 mg once daily

Parameter

Healthy
Subjects
(n=14)

HIV-Infected
Patients
(n=13)

Healthy
Subjects
(n=28)

HIV-Infected
Patients
(n=10)

Cmax (ng/mL)

Geometric mean (CV%)

5199 (26)

2298 (71)

6129 (31)

4422 (58)

Mean (SD)

5358 (1371)

3152 (2231)

6450 (2031)

5233 (3033)

Tmax (h)

Median

2.5

2.0

2.7

3.0

AUC (ng•h/mL)

Geometric mean (CV%)

28132 (28)

14874 (91)

57039 (37)

46073 (66)

Mean (SD)

29303 (8263)

22262 (20159)

61435 (22911)

53761 (35294)

T-half (h)

Mean (SD)

7.9 (2.9)

6.5 (2.6)

18.1 (6.2)a

8.6 (2.3)

Cmin (ng/mL)

Geometric mean (CV%)

159 (88)

120 (109)

1227 (53)

636 (97)

Mean (SD)

218 (191)

273 (298)b

1441 (757)

862 (838)

Figure 1 displays the mean plasma concentrations of atazanavir at steady state after REYATAZ 400 mg once daily (as two 200-mg capsules) with a light meal and after REYATAZ 300 mg (as two 150-mg capsules) with ritonavir 100 mg once daily with a light meal in HIV-infected adult patients.

Figure 1: Mean (SD) Steady-State Plasma Concentrations of Atazanavir 400 mg (n=13) and 300 mg with Ritonavir (n=10) for HIV-Infected Adult Patients

[Reyataz Fig 1]

Absorption

Atazanavir is rapidly absorbed with a Tmax of approximately 2.5 hours. Atazanavir demonstrates nonlinear pharmacokinetics with greater than dose-proportional increases in AUC and Cmax values over the dose range of 200 to 800 mg once daily. Steady state is achieved between Days 4 and 8, with an accumulation of approximately 2.3 fold.

Food Effect

Administration of REYATAZ with food enhances bioavailability and reduces pharmacokinetic variability. Administration of a single 400-mg dose of REYATAZ with a light meal (357 kcal, 8.2 g fat, 10.6 g protein) resulted in a 70% increase in AUC and 57% increase in Cmax relative to the fasting state. Administration of a single 400-mg dose of REYATAZ with a high-fat meal (721 kcal, 37.3 g fat, 29.4 g protein) resulted in a mean increase in AUC of 35% with no change in Cmax relative to the fasting state. Administration of REYATAZ with either a light meal or high-fat meal decreased the coefficient of variation of AUC and Cmax by approximately one-half compared to the fasting state.

Coadministration of a single 300-mg dose of REYATAZ and a 100-mg dose of ritonavir with a light meal (336 kcal, 5.1 g fat, 9.3 g protein) resulted in a 33% increase in the AUC and a 40% increase in both the Cmax and the 24-hour concentration of atazanavir relative to the fasting state. Coadministration with a high-fat meal (951 kcal, 54.7 g fat, 35.9 g protein) did not affect the AUC of atazanavir relative to fasting conditions and the Cmax was within 11% of fasting values. The 24-hour concentration following a high-fat meal was increased by approximately 33% due to delayed absorption; the median Tmaxincreased from 2.0 to 5.0 hours. Coadministration of REYATAZ with ritonavir with either a light or a high-fat meal decreased the coefficient of variation of AUC and Cmax by approximately 25% compared to the fasting state.

Distribution

Atazanavir is 86% bound to human serum proteins and protein binding is independent of concentration. Atazanavir binds to both alpha-1-acid glycoprotein (AAG) and albumin to a similar extent (89% and 86%, respectively). In a multiple-dose study in HIV-infected patients dosed with REYATAZ 400 mg once daily with a light meal for 12 weeks, atazanavir was detected in the cerebrospinal fluid and semen. The cerebrospinal fluid/plasma ratio for atazanavir (n=4) ranged between 0.0021 and 0.0226 and seminal fluid/plasma ratio (n=5) ranged between 0.11 and 4.42.

Metabolism

Atazanavir is extensively metabolized in humans. The major biotransformation pathways of atazanavir in humans consisted of monooxygenation and dioxygenation. Other minor biotransformation pathways for atazanavir or its metabolites consisted of glucuronidation, N-dealkylation, hydrolysis, and oxygenation with dehydrogenation. Two minor metabolites of atazanavir in plasma have been characterized. Neither metabolite demonstrated in vitro antiviral activity. In vitro studies using human liver microsomes suggested that atazanavir is metabolized by CYP3A.

Elimination

Following a single 400-mg dose of 14C-atazanavir, 79% and 13% of the total radioactivity was recovered in the feces and urine, respectively. Unchanged drug accounted for approximately 20% and 7% of the administered dose in the feces and urine, respectively. The mean elimination half-life of atazanavir in healthy volunteers (n=214) and HIV-infected adult patients (n=13) was approximately 7 hours at steady state following a dose of 400 mg daily with a light meal.

Specific Populations

Renal Impairment

In healthy subjects, the renal elimination of unchanged atazanavir was approximately 7% of the administered dose. REYATAZ has been studied in adult subjects with severe renal impairment (n=20), including those on hemodialysis, at multiple doses of 400 mg once daily. The mean atazanavir Cmaxwas 9% lower, AUC was 19% higher, and Cmin was 96% higher in subjects with severe renal impairment not undergoing hemodialysis (n=10), than in age-, weight-, and gender-matched subjects with normal renal function. In a 4-hour dialysis session, 2.1% of the administered dose was removed. When atazanavir was administered either prior to, or following hemodialysis (n=10), the geometric means for Cmax, AUC, and Cmin were approximately 25% to 43% lower compared to subjects with normal renal function. The mechanism of this decrease is unknown. REYATAZ is not recommended for use in HIV-treatment-experienced patients with end stage renal disease managed with hemodialysis [see DOSAGE AND ADMINISTRATION (2.6)].

Hepatic Impairment

REYATAZ has been studied in adult subjects with moderate-to-severe hepatic impairment (14 Child-Pugh B and 2 Child-Pugh C subjects) after a single 400-mg dose. The mean AUC(0-∞) was 42% greater in subjects with impaired hepatic function than in healthy volunteers. The mean half-life of atazanavir in hepatically impaired subjects was 12.1 hours compared to 6.4 hours in healthy volunteers. A dose reduction to 300 mg is recommended for patients with moderate hepatic impairment (Child-Pugh Class B) who have not experienced prior virologic failure as increased concentrations of atazanavir are expected. REYATAZ is not recommended for use in patients with severe hepatic impairment. The pharmacokinetics of REYATAZ in combination with ritonavir has not been studied in subjects with hepatic impairment; thus, coadministration of REYATAZ with ritonavir is not recommended for use in patients with any degree of hepatic impairment [see DOSAGE AND ADMINISTRATION (2.7)].

Pediatrics

The pharmacokinetic parameters for atazanavir at steady state in pediatric patients taking the powder formulation are summarized in Table 18 by weight ranges [see DOSAGE AND ADMINISTRATION (2.4)].

Table 18: Steady-State Pharmacokinetics of Atazanavir (powder formulation) with Ritonavir in HIV-Infected Pediatric Patients

Body Weight
(range in kg) [n]

atazanavir/ritonavir
Dose (mg)

Cmax ng/mL
Geometric Mean
(CV%)

AUC ng•h/mL
Geometric Mean
(CV%)

Cmin ng/mL
Geometric Mean
(CV%)

5 to <10 [20]

150/80

4131 (55%)

32503 (61%)

336 (76%)

5 to <10 [10]

200/80

4466 (59%)

39519 (54%)

550 (60%)

10 to <15 [18]

200/80

5197 (53%)

50305 (67%)

572 (111%)

15 to <25 [32]

250/80

5394 (46%)

55687 (45%)

686 (68%)

25 to <35 [8]

300/100

4209 (52%)

44329 (63%)

468 (104%)

The pharmacokinetic parameters for atazanavir at steady state in pediatric patients taking the capsule formulation were predicted by a population pharmacokinetic model and are summarized in Table 19 by weight ranges that correspond to the recommended doses [see DOSAGE AND ADMINISTRATION (2.3)].

Table 19: Predicted Steady-State Pharmacokinetics of Atazanavir (capsule formulation) with Ritonavir in HIV-Infected Pediatric Patients

Body Weight
(range in kg)

atazanavir/ritonavir
Dose (mg)

Cmax ng/mL
Geometric Mean
(CV%)

AUC ng•h/mL
Geometric Mean
(CV%)

Cmin ng/mL
Geometric Mean
(CV%)

15 to <20

150/100

5213 (78.7%)

42902 (77.0%)

504 (99.5%)

20 to <40

200/100

4954 (81.7%)

42999 (78.5%)

562 (98.9%)

≥40

300/100

5040 (84.6%)

46777 (80.6%)

691 (98.5%)

Pregnancy

The pharmacokinetic data from HIV-infected pregnant women receiving REYATAZ Capsules with ritonavir are presented in Table 20.

Table 20: Steady-State Pharmacokinetics of Atazanavir with Ritonavir in HIV-Infected Pregnant Women in the Fed State
a Available data during the 2nd trimester are limited.
b Atazanavir peak concentrations and AUCs were found to be approximately 28% to 43% higher during the postpartum period (4-12 weeks) than those observed historically in HIV-infected, non-pregnant patients. Atazanavir plasma trough concentrations were approximately 2.2-fold higher during the postpartum period when compared to those observed historically in HIV-infected, non-pregnant patients.
c Cmin is concentration 24 hours post-dose.

Atazanavir 300 mg with ritonavir 100 mg

Pharmacokinetic Parameter

2nd Trimester
(n=5a)

3rd Trimester
(n=20)

Postpartumb
(n=34)

Cmax ng/mL

Geometric mean (CV%)

3078.85

(50)

3291.46

(48)

5721.21

(31)

AUC ng•h/mL

Geometric mean (CV%)

27657.1

(43)

34251.5

(43)

61990.4

(32)

Cmin ng/mLc

Geometric mean (CV%)

538.70

(46)

668.48

(50)

1462.59

(45)

Drug Interaction Data

Atazanavir is a metabolism-dependent CYP3A inhibitor, with a Kinact value of 0.05 to 0.06 min−1 and Kivalue of 0.84 to 1.0 µM. Atazanavir is also a direct inhibitor for UGT1A1 (Ki=1.9 µM) and CYP2C8 (Ki=2.1 µM).

Atazanavir has been shown in vivo not to induce its own metabolism nor to increase the biotransformation of some drugs metabolized by CYP3A. In a multiple-dose study, REYATAZ decreased the urinary ratio of endogenous 6β-OH cortisol to cortisol versus baseline, indicating that CYP3A production was not induced.

Clinically significant interactions are not expected between atazanavir and substrates of CYP2C19, CYP2C9, CYP2D6, CYP2B6, CYP2A6, CYP1A2, or CYP2E1. Clinically significant interactions are not expected between atazanavir when administered with ritonavir and substrates of CYP2C8. See the complete prescribing information for ritonavir for information on other potential drug interactions with ritonavir.

Based on known metabolic profiles, clinically significant drug interactions are not expected between REYATAZ and dapsone, trimethoprim/sulfamethoxazole, azithromycin, or erythromycin. REYATAZ does not interact with substrates of CYP2D6 (eg, nortriptyline, desipramine, metoprolol).

Drug interaction studies were performed with REYATAZ and other drugs likely to be coadministered and some drugs commonly used as probes for pharmacokinetic interactions. The effects of coadministration of REYATAZ on the AUC, Cmax, and Cmin are summarized in Tables 21 and 22. Neither didanosine EC nor diltiazem had a significant effect on atazanavir exposures (see Table 22 for effect of atazanavir on didanosine EC or diltiazem exposures). REYATAZ did not have a significant effect on the exposures of didanosine (when administered as the buffered tablet), stavudine, or fluconazole. For information regarding clinical recommendations, see DRUG INTERACTIONS (7).

Table 21: Drug Interactions: Pharmacokinetic Parameters for Atazanavir in the Presence of Coadministered Drugsa
Coadministered
Drug Coadministered Drug
Dose/Schedule REYATAZ
Dose/Schedule Ratio (90% Confidence Interval) of Atazanavir
Pharmacokinetic Parameters with/without
Coadministered Drug;
No Effect = 1.00
Cmax AUC Cmin
a Data provided are under fed conditions unless otherwise noted.
b All drugs were given under fasted conditions.
c REYATAZ 300 mg plus ritonavir 100 mg once daily coadministered with famotidine 40 mg twice daily resulted in atazanavir geometric mean Cmax that was similar and AUC and Cmin values that were 1.79- and 4.46-fold higher relative to REYATAZ 400 mg once daily alone.
d Similar results were noted when famotidine 20 mg BID was administered 2 hours after and 10 hours before atazanavir 300 mg and ritonavir 100 mg plus tenofovir 300 mg.
e Atazanavir/ritonavir/tenofovir was administered after a light meal.
f Study was conducted in HIV-infected individuals.
g Compared with atazanavir 400 mg historical data without nevirapine (n=13), the ratio of geometric means (90% confidence intervals) for Cmax, AUC, and Cmin were 1.42 (0.98, 2.05), 1.64 (1.11, 2.42), and 1.25 (0.66, 2.36), respectively, for atazanavir/ritonavir 300/100 mg; and 2.02 (1.42, 2.87), 2.28 (1.54, 3.38), and 1.80 (0.94, 3.45), respectively, for atazanavir/ritonavir 400/100 mg.
h Parallel group design; n=23 for atazanavir/ritonavir plus nevirapine, n=22 for atazanavir 300 mg/ritonavir 100 mg without nevirapine. Subjects were treated with nevirapine prior to study entry.
i Omeprazole 40 mg was administered on an empty stomach 2 hours before REYATAZ.
j Omeprazole 20 mg was administered 30 minutes prior to a light meal in the morning and REYATAZ 300 mg plus ritonavir 100 mg in the evening after a light meal, separated by 12 hours from omeprazole.
k REYATAZ 300 mg plus ritonavir 100 mg once daily separated by 12 hours from omeprazole 20 mg daily resulted in increases in atazanavir geometric mean AUC (10%) and Cmin (2.4-fold), with a decrease in Cmax (29%) relative to REYATAZ 400 mg once daily in the absence of omeprazole (study days 1–6).
l Omeprazole 20 mg was given 30 minutes prior to a light meal in the morning and REYATAZ 400 mg plus ritonavir 100 mg once daily after a light meal, 1 hour after omeprazole. Effects on atazanavir concentrations were similar when REYATAZ 400 mg plus ritonavir 100 mg was separated from omeprazole 20 mg by 12 hours.
m REYATAZ 400 mg plus ritonavir 100 mg once daily administered with omeprazole 20 mg once daily resulted in increases in atazanavir geometric mean AUC (32%) and Cmin (3.3-fold), with a decrease in Cmax (26%) relative to REYATAZ 400 mg once daily in the absence of omeprazole (study days 1–6).
n Compared with atazanavir 400 mg QD historical data, administration of atazanavir/ritonavir 300/100 mg QD increased the atazanavir geometric mean values of Cmax, AUC, and Cmin by 18%, 103%, and 671%, respectively.
o Note that similar results were observed in studies where administration of tenofovir and REYATAZ was separated by 12 hours.
p Ratio of atazanavir plus ritonavir plus tenofovir to atazanavir plus ritonavir. Atazanavir 300 mg plus ritonavir 100 mg results in higher atazanavir exposure than atazanavir 400 mg (see footnote o). The geometric mean values of atazanavir pharmacokinetic parameters when coadministered with ritonavir and tenofovir were: Cmax = 3190 ng/mL, AUC = 34459 ng•h/mL, and Cmin = 491 ng/mL. Study was conducted in HIV-infected individuals.
NA = not available.

atenolol

50 mg QD, d 7–11 (n=19)
and d 19–23

400 mg QD, d 1–11
(n=19)

1.00
(0.89, 1.12)

0.93
(0.85, 1.01)

0.74
(0.65, 0.86)

boceprevir

800 mg TID, d 1–6, 25–31

300 mg QD/ritonavir 100 mg QD,
d 10–31

atazanavir: 0.75
(0.64-0.88)
ritonavir: 0.73
(0.64-0.83)

atazanavir: 0.65
(0.55-0.78)
ritonavir: 0.64
(0.58-0.72)

atazanavir: 0.51
(0.44-0.61)
ritonavir: 0.55
(0.45-0.67)

clarithromycin

500 mg BID, d 7–10 (n=29)
and d 18–21

400 mg QD, d 1–10
(n=29)

1.06
(0.93, 1.20)

1.28
(1.16, 1.43)

1.91
(1.66, 2.21)

didanosine (ddI) (buffered tablets) plus stavudine (d4T)b

ddI: 200 mg × 1 dose,
d4T: 40 mg × 1 dose (n=31)

400 mg × 1 dose simultaneously with ddI and d4T
(n=31)

0.11
(0.06, 0.18)

0.13
(0.08, 0.21)

0.16
(0.10, 0.27)

ddI: 200 mg × 1 dose,
d4T: 40 mg × 1 dose (n=32)

400 mg × 1 dose 1 h after ddI + d4T
(n=32)

1.12
(0.67, 1.18)

1.03
(0.64, 1.67)

1.03
(0.61, 1.73)

efavirenz

600 mg QD, d 7–20
(n=27)

400 mg QD, d 1–20
(n=27)

0.41
(0.33, 0.51)

0.26
(0.22, 0.32)

0.07
(0.05, 0.10)

600 mg QD, d 7–20

(n=13)

400 mg QD, d 1–6 (n=23)
then 300 mg/ritonavir 100 mg QD,
2 h before efavirenz, d 7–20
(n=13)

1.14
(0.83, 1.58)

1.39
(1.02, 1.88)

1.48
(1.24, 1.76)

600 mg QD, d 11–24 (pm)
(n=14)

300 mg QD/ritonavir 100 mg QD,
d 1–10 (pm) (n=22),
then 400 mg QD/ritonavir 100 mg QD, d 11–24 (pm), (simultaneously with efavirenz)
(n=14)

1.17
(1.08, 1.27)

1.00
(0.91, 1.10)

0.58
(0.49, 0.69)

famotidine

40 mg BID, d 7–12
(n=15)

400 mg QD, d 1–6 (n=45), d 7–12 (simultaneous administration)
(n=15)

0.53
(0.34, 0.82)

0.59
(0.40, 0.87)

0.58
(0.37, 0.89)

40 mg BID, d 7–12
(n=14)

400 mg QD (pm), d 1–6 (n=14),
d 7–12 (10 h after, 2 h before famotidine)
(n=14)

1.08
(0.82, 1.41)

0.95
(0.74, 1.21)

0.79
(0.60, 1.04)

40 mg BID, d 11–20
(n=14)c

300 mg QD/ritonavir 100 mg QD,
d 1–10 (n=46),
d 11–20d(simultaneous administration)
(n=14)

0.86
(0.79, 0.94)

0.82
(0.75, 0.89)

0.72
(0.64, 0.81)

20 mg BID, d 11–17
(n=18)

300 mg QD/ritonavir 100 mg QD/tenofovir 300 mg QD,
d 1–10 (am) (n=39),
d 11–17 (am) (simultaneous administration with am famotidine) (n=18)d,e

0.91
(0.84, 0.99)

0.90
(0.82, 0.98)

0.81
(0.69, 0.94)

40 mg QD (pm), d 18–24
(n=20)

300 mg QD/ritonavir 100 mg QD/tenofovir 300 mg QD,
d 1–10 (am)
(n=39),
d 18–24 (am) (12 h after pm famotidine)
(n=20)e

0.89
(0.81, 0.97)

0.88
(0.80, 0.96)

0.77
(0.63, 0.93)

40 mg BID, d 18–24
(n=18)

300 mg QD/ritonavir 100 mg QD/tenofovir 300 mg QD, d 1–10 (am) (n=39),
d 18–24 (am) (10 h after pm famotidine and 2 h before am famotidine) (n=18)e

0.74
(0.66, 0.84)

0.79
(0.70, 0.88)

0.72
(0.63, 0.83)

40 mg BID, d 11–20
(n=15)

300 mg QD/ritonavir 100 mg QD, d 1–10 (am) (n=46),
then 400 mg QD/ritonavir 100 mg QD, d 11–20 (am) (n=15)

1.02
(0.87, 1.18)

1.03
(0.86, 1.22)

0.86
(0.68, 1.08)

ketoconazole

200 mg QD, d 7–13
(n=14)

400 mg QD, d 1–13
(n=14)

0.99
(0.77, 1.28)

1.10
(0.89, 1.37)

1.03
(0.53, 2.01)

nevirapinef,g

200 mg BID, d 1–23
(n=23)

300 mg QD/ritonavir 100 mg QD,
d 4–13, then
400 mg QD/ritonavir 100 mg QD, d 14–23 (n=23)h

0.72
(0.60, 0.86)
1.02
(0.85, 1.24)

0.58
(0.48, 0.71)
0.81
(0.65, 1.02)

0.28
(0.20, 0.40)
0.41
(0.27, 0.60)

omeprazole

40 mg QD, d 7–12
(n=16)i

400 mg QD,
d 1–6 (n=48),
d 7–12 (n=16)

0.04
(0.04, 0.05)

0.06
(0.05, 0.07)

0.05
(0.03, 0.07)

40 mg QD, d 11
–20
(n=15)i

300 mg QD/ritonavir 100 mg QD,
d 1–20 (n=15)

0.28
(0.24, 0.32)

0.24
(0.21, 0.27)

0.22
(0.19, 0.26)

20 mg QD, d 17–23 (am)
(n=13)

300 mg QD/ritonavir 100 mg QD,
d 7–16 (pm) (n=27),
d 17–23 (pm) (n=13)j,k

0.61
(0.46, 0.81)

0.58
(0.44, 0.75)

0.54
(0.41, 0.71)

20 mg QD, d 17–23 (am)
(n=14)

300 mg QD/ritonavir 100 mg QD,
d 7–16 (am) (n=27), then
400 mg QD/ritonavir 100 mg QD, d 17–23 (am) (n=14)l,m

0.69
(0.58, 0.83)

0.70
(0.57, 0.86)

0.69
(0.54, 0.88)

pitavastatin

4 mg QD

for 5 days

300 mg QD for 5 days

1.13
(0.96, 1.32)

1.06
(0.90, 1.26)

NA

rifabutin

150 mg QD, d 15–28
(n=7)

400 mg QD, d 1–28
(n=7)

1.34
(1.14, 1.59)

1.15
(0.98, 1.34)

1.13
(0.68, 1.87)

rifampin

600 mg QD, d 17–26
(n=16)

300 mg QD/ritonavir 100 mg QD,
d 7–16 (n=48),
d 17–26 (n=16)

0.47
(0.41, 0.53)

0.28
(0.25, 0.32)

0.02
(0.02, 0.03)

ritonavirn

100 mg QD, d 11–20
(n=28)

300 mg QD, d 1–20
(n=28)

1.86
(1.69, 2.05)

3.38
(3.13, 3.63)

11.89
(10.23, 13.82)

tenofoviro

300 mg QD, d 9–16
(n=34)

400 mg QD, d 2–16
(n=34)

0.79

(0.73, 0.86)

0.75

(0.70, 0.81)

0.60

(0.52, 0.68)

300 mg QD, d 15–42
(n=10)

300 mg/ritonavir 100 mg QD, d 1–42
(n=10)

0.72p
(0.50, 1.05)

0.75q
(0.58, 0.97)

0.77q
(0.54, 1.10)

voriconazole
(Subjects with at least one functional CYP2C19 allele)

200 mg BID, d 2–3, 22–30;
400 mg BID, d 1, 21
(n=20)

300 mg/ritonavir 100 mg QD, d 11–30
(n=20)

0.87
(0.80, 0.96)

0.88
(0.82, 0.95)

0.80
(0.72, 0.90)

voriconazole
(Subjects without a functional CYP2C19 allele)

50 mg BID, d 2–3, 22–30;
100 mg BID, d 1, 21
(n=8)

300 mg/ritonavir 100 mg QD, d 11–30
(n=8)

0.81
(0.66, 1.00)

0.80
(0.65, 0.97)

0.69
(0.54, 0.87)

Table 22: Drug Interactions: Pharmacokinetic Parameters for Coadministered Drugs in the Presence of REYATAZa
Coadministered
Drug Coadministered Drug
Dose/Schedule REYATAZ
Dose/Schedule Ratio (90% Confidence Interval) of Coadministered Drug Pharmacokinetic Parameters with/without
REYATAZ;
No Effect = 1.00
Cmax AUC Cmin
a Data provided are under fed conditions unless otherwise noted.
b 400 mg ddI EC and REYATAZ were administered together with food on Days 8 and 19.
c Upon further dose normalization of ethinyl estradiol 25 mcg with atazanavir relative to ethinyl estradiol 35 mcg without atazanavir, the ratio of geometric means (90% confidence intervals) for Cmax, AUC, and Cmin were 0.82 (0.73, 0.92), 1.06 (0.95, 1.17), and 1.35 (1.11, 1.63), respectively.
d Upon further dose normalization of ethinyl estradiol 35 mcg with atazanavir/ritonavir relative to ethinyl estradiol 25 mcg without atazanavir/ritonavir, the ratio of geometric means (90% confidence intervals) for Cmax, AUC, and Cmin were 1.17 (1.03, 1.34), 1.13 (1.05, 1.22), and 0.88 (0.77, 1.00), respectively.
e All subjects were on a 28 day lead-in period; one full cycle of Ortho Tri-Cyclen®. Ortho Tri-Cyclen® contains 35 mcg of ethinyl estradiol. Ortho Tri-Cyclen® LO contains 25 mcg of ethinyl estradiol. Results were dose normalized to an ethinyl estradiol dose of 35 mcg.
f 17-deacetyl norgestimate is the active component of norgestimate.
g (R)-methadone is the active isomer of methadone.
h Study was conducted in HIV-infected individuals.
i Subjects were treated with nevirapine prior to study entry.
j Omeprazole was used as a metabolic probe for CYP2C19. Omeprazole was given 2 hours after REYATAZ on Day 7; and was given alone 2 hours after a light meal on Day 20.
k Not the recommended therapeutic dose of atazanavir.
l When compared to rifabutin 150 mg QD alone d1–10 (n=14). Total of rifabutin + 25-O-desacetyl-rifabutin: AUC 2.19 (1.78, 2.69).
m Rosiglitazone used as a probe substrate for CYP2C8.
n Mean ratio (with/without coadministered drug). ↑ indicates an increase in rosuvastatin exposure.
o The combination of atazanavir and saquinavir 1200 mg QD produced daily saquinavir exposures similar to the values produced by the standard therapeutic dosing of saquinavir at 1200 mg TID. However, the Cmax is about 79% higher than that for the standard dosing of saquinavir (soft gelatin capsules) alone at 1200 mg TID.
p Note that similar results were observed in a study where administration of tenofovir and REYATAZ was separated by 12 hours.
q Administration of tenofovir and REYATAZ was temporally separated by 12 hours.
NA = not available.

acetaminophen

1 gm BID, d 1–20
(n=10)

300 mg QD/ritonavir 100 mg QD,
d 11–20 (n=10)

0.87
(0.77, 0.99)

0.97
(0.91, 1.03)

1.26
(1.08, 1.46)

atenolol

50 mg QD, d 7–11 (n=19)
and d 19–23

400 mg QD, d 1–11
(n=19)

1.34
(1.26, 1.42)

1.25
(1.16, 1.34)

1.02
(0.88, 1.19)

boceprevir

800 mg TID,

d 1–6, 25–31

300 mg QD/ritonavir 100 mg QD,
d 10–31

0.93
(0.80, 1.08)

0.95
(0.87, 1.05)

0.82
(0.68, 0.98)

clarithromycin

500 mg BID, d 7–10 (n=21)
and d 18–21

400 mg QD, d 1–10
(n=21)

1.50
(1.32, 1.71)
OH-clarithromycin:
0.28
(0.24, 0.33)

1.94
(1.75, 2.16)
OH-clarithromycin:
0.30
(0.26, 0.34)

2.60
(2.35, 2.88)
OH-clarithromycin:
0.38
(0.34, 0.42)

ddI (enteric-coated [EC] capsules)b

400 mg d 1 (fasted), d 8 (fed)
(n=34)

400 mg QD,
d 2–8
(n=34)

0.64
(0.55, 0.74)

0.66
(0.60, 0.74)

1.13
(0.91, 1.41)

400 mg d 1 (fasted), d 19 (fed)
(n=31)

300 mg QD/ritonavir 100 mg QD, d 9–19
(n=31)

0.62
(0.52, 0.74)

0.66
(0.59, 0.73)

1.25
(0.92, 1.69)

diltiazem

180 mg QD, d 7–11 (n=28)
and d 19–23

400 mg QD, d 1–11
(n=28)

1.98
(1.78, 2.19)
desacetyl-diltiazem:
2.72
(2.44, 3.03)

2.25
(2.09, 2.16)
desacetyl-diltiazem:
2.65
(2.45, 2.87)

2.42
(2.14, 2.73)
desacetyl-diltiazem:
2.21
(2.02, 2.42)

ethinyl estradiol & norethindronec

Ortho-Novum®7/7/7 QD, d 1–29
(n=19)

400 mg QD,
d 16–29
(n=19)

ethinyl estradiol: 1.15
(0.99, 1.32)
norethindrone: 1.67
(1.42, 1.96)

ethinyl estradiol: 1.48
(1.31, 1.68)
norethindrone: 2.10
(1.68, 2.62)

ethinyl estradiol: 1.91
(1.57, 2.33)
norethindrone: 3.62
(2.57, 5.09)

ethinyl estradiol & norgestimated

Ortho Tri-Cyclen® QD, d 1–28 (n=18),
then Ortho Tri-Cyclen® LO QD, d 29–42e
(n=14)

300 mg QD/ritonavir 100 mg QD,
d 29–42
(n=14)

ethinyl estradiol:
0.84
(0.74, 0.95)
17-deacetyl norgestimate:f
1.68
(1.51, 1.88)

ethinyl estradiol:
0.81
(0.75, 0.87)
17-deacetyl
norgestimate:f
1.85
(1.67, 2.05)

ethinyl estradiol:
0.63
(0.55, 0.71)
17-deacetyl norgestimate:f
2.02
(1.77, 2.31)

methadone

Stable maintenance

dose, d 1–15
(n=16)

400 mg QD, d 2–15
(n=16)

(R)-methadoneg
0.91
(0.84, 1.0)
total: 0.85
(0.78, 0.93)

(R)-methadoneg
1.03
(0.95, 1.10)
total: 0.94
(0.87, 1.02)

(R)-methadoneg
1.11
(1.02, 1.20)
total: 1.02
(0.93, 1.12)

nevirapineh,i

200 mg BID, d 1–23
(n=23)

300 mg QD/ritonavir 100 mg QD,
d 4–13, then
400 mg QD/ritonavir 100 mg QD,
d 14–23
(n=23)

1.17
(1.09, 1.25)
1.21
(1.11, 1.32)

1.25
(1.17, 1.34)
1.26
(1.17, 1.36)

1.32
(1.22, 1.43)
1.35
(1.25, 1.47)

omeprazolej

40 mg single dose, d 7 and d 20
(n=16)

400 mg QD, d 1–12
(n=16)

1.24
(1.04, 1.47)

1.45
(1.20, 1.76)

NA

rifabutin

300 mg QD, d 1–10
then 150 mg QD, d 11–20
(n=3)

600 mg QD,k
d 11–20
(n=3)

1.18
(0.94, 1.48)
25-O-desacetyl-rifabutin: 8.20
(5.90, 11.40)

2.10
(1.57, 2.79)
25-O-desacetyl-rifabutin: 22.01
(15.97, 30.34)

3.43
(1.98, 5.96)
25-O-desacetyl-rifabutin: 75.6
(30.1, 190.0)

150 mg twice weekly, d 1–15
(n=7)

300 mg QD/ritonavir 100 mg QD,
d 1–17
(n=7)

2.49l
(2.03, 3.06)
25-O-desacetyl-rifabutin: 7.77
(6.13, 9.83)

1.48l
(1.19, 1.84)
25-O-desacetyl-rifabutin: 10.90
(8.14, 14.61)

1.40l
(1.05, 1.87)
25-O-desacetyl-rifabutin: 11.45
(8.15, 16.10)

pitavastatin

4 mg QD
for 5 days

300 mg QD
for 5 days

1.60
(1.39, 1.85)

1.31
(1.23, 1.39)

NA

rosiglitazonem

4 mg single dose, d 1, 7, 17
(n=14)

400 mg QD, d 2–7, then
300 mg QD/ritonavir 100 mg QD,
d 8–17
(n=14)

1.08
(1.03, 1.13)
0.97
(0.91, 1.04)

1.35
(1.26, 1.44)
0.83
(0.77, 0.89)

NA
NA

rosuvastatin

10 mg single dose

300 mg QD/ritonavir 100 mg QD for 7 days

↑ 7-foldn

↑ 3-foldn

NA

saquinaviro(soft gelatin capsules)

1200 mg QD, d 1–13
(n=7)

400 mg QD, d 7–13
(n=7)

4.39
(3.24, 5.95)

5.49
(4.04, 7.47)

6.86
(5.29, 8.91)

tenofovirp

300 mg QD, d 9–16 (n=33)
and d 24–30
(n=33)

400 mg QD, d 2–16
(n=33)

1.14
(1.08, 1.20)

1.24
(1.21, 1.28)

1.22
(1.15, 1.30)

300 mg QD, d 1–7 (pm) (n=14)
d 25–34 (pm) (n=12)

300 mg QD/ritonavir 100 mg QD, d 25–34 (am)
(n=12)q

1.34
(1.20, 1.51)

1.37
(1.30, 1.45)

1.29
(1.21, 1.36)

voriconazole
(Subjects with at least one functional CYP2C19 allele)

200 mg BID, d 2–3, 22–30; 400 mg BID, d 1, 21
(n=20)

300 mg/ritonavir 100 mg QD, d 11–30
(n=20)

0.90
(0.78, 1.04)

0.67
(0.58, 0.78)

0.61
(0.51, 0.72)

voriconazole
(Subjects without a functional CYP2C19 allele)

50 mg BID, d 2–3, 22–30; 100 mg BID, d 1, 21
(n=8)

300 mg/ritonavir 100 mg QD, d 11–30
(n=8)

4.38
(3.55, 5.39)

5.61
(4.51, 6.99)

7.65
(5.71, 10.2)

lamivudine + zidovudine

150 mg lamivudine + 300 mg zidovudine BID, d 1–12
(n=19)

400 mg QD, d 7–12
(n=19)

lamivudine: 1.04
(0.92, 1.16)
zidovudine: 1.05
(0.88, 1.24)
zidovudine
glucuronide: 0.95
(0.88, 1.02)

lamivudine: 1.03
(0.98, 1.08)
zidovudine: 1.05
(0.96, 1.14)
zidovudine glucuronide: 1.00
(0.97, 1.03)

lamivudine: 1.12
(1.04, 1.21)
zidovudine: 0.69
(0.57, 0.84)
zidovudine glucuronide: 0.82
(0.62, 1.08)

12.4 Microbiology

Mechanism of Action

Atazanavir (ATV) is an azapeptide HIV-1 protease inhibitor (PI). The compound selectively inhibits the virus-specific processing of viral Gag and Gag-Pol polyproteins in HIV-1 infected cells, thus preventing formation of mature virions.

Antiviral Activity in Cell Culture

Atazanavir exhibits anti-HIV-1 activity with a mean 50% effective concentration (EC50) in the absence of human serum of 2 to 5 nM against a variety of laboratory and clinical HIV-1 isolates grown in peripheral blood mononuclear cells, macrophages, CEM-SS cells, and MT-2 cells. ATV has activity against HIV-1 Group M subtype viruses A, B, C, D, AE, AG, F, G, and J isolates in cell culture. ATV has variable activity against HIV-2 isolates (1.9-32 nM), with EC50 values above the EC50 values of failure isolates. Two-drug combination antiviral activity studies with ATV showed no antagonism in cell culture with NNRTIs (delavirdine, efavirenz, and nevirapine), PIs (amprenavir, indinavir, lopinavir, nelfinavir, ritonavir, and saquinavir), NRTIs (abacavir, didanosine, emtricitabine, lamivudine, stavudine, tenofovir, zalcitabine, and zidovudine), the HIV-1 fusion inhibitor enfuvirtide, and two compounds used in the treatment of viral hepatitis, adefovir and ribavirin, without enhanced cytotoxicity.

Resistance

In Cell Culture: HIV-1 isolates with a decreased susceptibility to ATV have been selected in cell culture and obtained from patients treated with ATV or atazanavir/ritonavir (ATV/RTV). HIV-1 isolates with 93- to 183-fold reduced susceptibility to ATV from three different viral strains were selected in cell culture by 5 months. The substitutions in these HIV-1 viruses that contributed to ATV resistance include I50L, N88S, I84V, A71V, and M46I. Changes were also observed at the protease cleavage sites following drug selection. Recombinant viruses containing the I50L substitution without other major PI substitutions were growth impaired and displayed increased susceptibility in cell culture to other PIs (amprenavir, indinavir, lopinavir, nelfinavir, ritonavir, and saquinavir). The I50L and I50V substitutions yielded selective resistance to ATV and amprenavir, respectively, and did not appear to be cross-resistant.

Clinical Studies of Treatment-Naive Patients: Comparison of Ritonavir-Boosted REYATAZ vs. Unboosted REYATAZ: Study AI424-089 compared REYATAZ 300 mg once daily with ritonavir 100 mg vs. REYATAZ 400 mg once daily when administered with lamivudine and extended-release stavudine in HIV-infected treatment-naive patients. A summary of the number of virologic failures and virologic failure isolates with ATV resistance in each arm is shown in Table 23.

Table 23: Summary of Virologic Failuresa at Week 96 in Study AI424-089: Comparison of Ritonavir Boosted REYATAZ vs. Unboosted REYATAZ: Randomized Patients
a Virologic failure includes patients who were never suppressed through Week 96 and on study at Week 96, had virologic rebound or discontinued due to insufficient viral load response.
b Percentage of Virologic Failure Isolates with genotypic and phenotypic data.
c Mixture of I50I/L emerged in 2 other ATV 400 mg-treated patients. Neither isolate was phenotypically resistant to ATV.

REYATAZ 300 mg
+
ritonavir 100 mg
(n=95)

REYATAZ 400 mg
(n=105)

Virologic Failure (≥50 copies/mL) at Week 96

15 (16%)

34 (32%)

Virologic Failure with Genotypes and Phenotypes Data

5

17

Virologic Failure Isolates with ATV-resistance at Week 96

0/5 (0%)b

4/17 (24%)b

Virologic Failure Isolates with I50L Emergence at Week 96c

0/5 (0%)b

2/17 (12%)b

Virologic Failure Isolates with Lamivudine Resistance at Week 96

2/5 (40%)b

11/17 (65%)b

Clinical Studies of Treatment-Naive Patients Receiving REYATAZ 300 mg with Ritonavir 100 mg: In Phase III study AI424-138, an as-treated genotypic and phenotypic analysis was conducted on samples from patients who experienced virologic failure (HIV-1 RNA ≥400 copies/mL) or discontinued before achieving suppression on ATV/RTV (n=39; 9%) and LPV/RTV (n=39; 9%) through 96 weeks of treatment. In the ATV/RTV arm, one of the virologic failure isolates had a 56-fold decrease in ATV susceptibility emerge on therapy with the development of PI resistance-associated substitutions L10F, V32I, K43T, M46I, A71I, G73S, I85I/V, and L90M. The NRTI resistance-associated substitution M184V also emerged on treatment in this isolate conferring emtricitabine resistance. Two ATV/RTV-virologic failure isolates had baseline phenotypic ATV resistance and IAS-defined major PI resistance-associated substitutions at baseline. The I50L substitution emerged on study in one of these failure isolates and was associated with a 17-fold decrease in ATV susceptibility from baseline and the other failure isolate with baseline ATV resistance and PI substitutions (M46M/I and I84I/V) had additional IAS-defined major PI substitutions (V32I, M46I, and I84V) emerge on ATV treatment associated with a 3-fold decrease in ATV susceptibility from baseline. Five of the treatment failure isolates in the ATV/RTV arm developed phenotypic emtricitabine resistance with the emergence of either the M184I (n=1) or the M184V (n=4) substitution on therapy and none developed phenotypic tenofovir disoproxil resistance. In the LPV/RTV arm, one of the virologic failure patient isolates had a 69-fold decrease in LPV susceptibility emerge on therapy with the development of PI substitutions L10V, V11I, I54V, G73S, and V82A in addition to baseline PI substitutions L10L/I, V32I, I54I/V, A71I, G73G/S, V82V/A, L89V, and L90M. Six LPV/RTV virologic failure isolates developed the M184V substitution and phenotypic emtricitabine resistance and two developed phenotypic tenofovir disoproxil resistance.

Clinical Studies of Treatment-Naive Patients Receiving REYATAZ 400 mg without Ritonavir: ATV-resistant clinical isolates from treatment-naive patients who experienced virologic failure on REYATAZ 400 mg treatment without ritonavir often developed an I50L substitution (after an average of 50 weeks of ATV therapy), often in combination with an A71V substitution, but also developed one or more other PI substitutions (eg, V32I, L33F, G73S, V82A, I85V, or N88S) with or without the I50L substitution. In treatment-naive patients, viral isolates that developed the I50L substitution, without other major PI substitutions, showed phenotypic resistance to ATV but retained in cell culture susceptibility to other PIs (amprenavir, indinavir, lopinavir, nelfinavir, ritonavir, and saquinavir); however, there are no clinical data available to demonstrate the effect of the I50L substitution on the efficacy of subsequently administered PIs.

Clinical Studies of Treatment-Experienced Patients: In studies of treatment-experienced patients treated with ATV or ATV/RTV, most ATV-resistant isolates from patients who experienced virologic failure developed substitutions that were associated with resistance to multiple PIs and displayed decreased susceptibility to multiple PIs. The most common protease substitutions to develop in the viral isolates of patients who failed treatment with ATV 300 mg once daily and RTV 100 mg once daily (together with tenofovir and an NRTI) included V32I, L33F/V/I, E35D/G, M46I/L, I50L, F53L/V, I54V, A71V/T/I, G73S/T/C, V82A/T/L, I85V, and L89V/Q/M/T. Other substitutions that developed on ATV/RTV treatment including E34K/A/Q, G48V, I84V, N88S/D/T, and L90M occurred in less than 10% of patient isolates. Generally, if multiple PI resistance substitutions were present in the HIV-1 virus of the patient at baseline, ATV resistance developed through substitutions associated with resistance to other PIs and could include the development of the I50L substitution. The I50L substitution has been detected in treatment-experienced patients experiencing virologic failure after long-term treatment. Protease cleavage site changes also emerged on ATV treatment but their presence did not correlate with the level of ATV resistance.

Clinical Studies of Pediatric Subjects in AI424-397 (PRINCE I) and AI424-451 (PRINCE II): Treatment-emergent ATV/RTV resistance-associated amino acid substitution M36I in the protease was detected in the virus of one subject among treatment failures in AI424-397. In addition, three known resistance-associated substitutions for other PIs arose in the viruses from one subject each (L19I/R, H69K/R, and I72I/V). Reduced susceptibility to ATV, RTV, or ATV/RTV was not seen with these viruses. In AI424-451, ATV/RTV resistance-associated substitutions G16E, V82A/I/T, I84V, and/or L90M arose in the viruses of two subjects. The virus population harboring the M46M/V, V82V/I, I84I/V, and L90L/M substitutions acquired phenotypic resistance to RTV (RTV phenotypic fold-change of 3.5, with a RTV cutoff of 2.5-fold change). However, these substitutions did not result in phenotypic resistance to ATV (ATV phenotypic fold-change of <1.8, with an ATV cutoff of 2.2-fold change). Secondary PI resistance-associated amino acid substitutions also arose in the viruses of one subject each, including V11V/I, D30D/G, E35E/D, K45K/R, L63P/S, and I72I/T. Q61D and Q61E/G emerged in the viruses of two subjects who failed treatment with ATV/RTV. Viruses from nine subjects in the two studies developed NRTI resistance-associated substitutions: K65K/R (n=1), M184V (n=7), and T215I (n=1).

Cross-Resistance

Cross-resistance among PIs has been observed. Baseline phenotypic and genotypic analyses of clinical isolates from ATV clinical trials of PI-experienced patients showed that isolates cross-resistant to multiple PIs were cross-resistant to ATV. Greater than 90% of the isolates with substitutions that included I84V or G48V were resistant to ATV. Greater than 60% of isolates containing L90M, G73S/T/C, A71V/T, I54V, M46I/L, or a change at V82 were resistant to ATV, and 38% of isolates containing a D30N substitution in addition to other changes were resistant to ATV. Isolates resistant to ATV were also cross-resistant to other PIs with >90% of the isolates resistant to indinavir, lopinavir, nelfinavir, ritonavir, and saquinavir, and 80% resistant to amprenavir. In treatment-experienced patients, PI-resistant viral isolates that developed the I50L substitution in addition to other PI resistance-associated substitution were also cross-resistant to other PIs.

Baseline Genotype/Phenotype and Virologic Outcome Analyses

Genotypic and/or phenotypic analysis of baseline virus may aid in determining ATV susceptibility before initiation of ATV/RTV therapy. An association between virologic response at 48 weeks and the number and type of primary PI resistance-associated substitutions detected in baseline HIV-1 isolates from antiretroviral-experienced patients receiving ATV/RTV once daily or lopinavir (LPV)/RTV twice daily in Study AI424-045 is shown in Table 24.

Overall, both the number and type of baseline PI substitutions affected response rates in treatment-experienced patients. In the ATV/RTV group, patients had lower response rates when 3 or more baseline PI substitutions, including a substitution at position 36, 71, 77, 82, or 90, were present compared to patients with 1–2 PI substitutions, including one of these substitutions.

Table 24: HIV RNA Response by Number and Type of Baseline PI Substitution, Antiretroviral-Experienced Patients in Study AI424-045, As-Treated Analysis
a Primary substitutions include any change at D30, V32, M36, M46, I47, G48, I50, I54, A71, G73, V77, V82, I84, N88, and L90.
b Results should be interpreted with caution because the subgroups were small.
c There were insufficient data (n<3) for PI substitutions V32I, I47V, G48V, I50V, and F53L.

Virologic Response = HIV RNA <400 copies/mLb

Number and Type of Baseline PI
Substitutionsa

ATV/RTV
(n=110)

LPV/RTV
(n=113)

3 or more primary PI substitutions includingc:

D30N

75% (6/8)

50% (3/6)

M36I/V

19% (3/16)

33% (6/18)

M46I/L/T

24% (4/17)

23% (5/22)

I54V/L/T/M/A

31% (5/16)

31% (5/16)

A71V/T/I/G

34% (10/29)

39% (12/31)

G73S/A/C/T

14% (1/7)

38% (3/8)

V77I

47% (7/15)

44% (7/16)

V82A/F/T/S/I

29% (6/21)

27% (7/26)

I84V/A

11% (1/9)

33% (2/6)

N88D

63% (5/8)

67% (4/6)

L90M

10% (2/21)

44% (11/25)

Number of baseline primary PI substitutionsa

All patients, as-treated

58% (64/110)

59% (67/113)

0–2 PI substitutions

75% (50/67)

75% (50/67)

3–4 PI substitutions

41% (14/34)

43% (12/28)

5 or more PI substitutions

0% (0/9)

28% (5/18)

The response rates of antiretroviral-experienced patients in Study AI424-045 were analyzed by baseline phenotype (shift in susceptibility in cell culture relative to reference, Table 25). The analyses are based on a select patient population with 62% of patients receiving an NNRTI-based regimen before study entry compared to 35% receiving a PI-based regimen. Additional data are needed to determine clinically relevant break points for REYATAZ.

Table 25: Baseline Phenotype by Outcome, Antiretroviral-Experienced Patients in Study AI424-045, As-Treated Analysis
Virologic Response = HIV RNA <400 copies/mLb
Baseline Phenotypea ATV/RTV
(n=111) LPV/RTV
(n=111)
a Fold change susceptibility in cell culture relative to the wild-type reference.
b Results should be interpreted with caution because the subgroups were small.

13 NONCLINICAL TOXICOLOGY

13.1 Carcinogenesis, Mutagenesis, Impairment of Fertility

Carcinogenesis

Long-term carcinogenicity studies in mice and rats were carried out with atazanavir for two years. In the mouse study, drug-related increases in hepatocellular adenomas were found in females at 360 mg/kg/day. The systemic drug exposure (AUC) at the NOAEL (no observable adverse effect level) in females, (120 mg/kg/day) was 2.8 times and in males (80 mg/kg/day) was 2.9 times higher than those in humans at the clinical dose (300 mg/day atazanavir boosted with 100 mg/day ritonavir, non-pregnant patients). In the rat study, no drug-related increases in tumor incidence were observed at doses up to 1200 mg/kg/day, for which AUCs were 1.1 (males) or 3.9 (females) times those measured in humans at the clinical dose.

Mutagenesis

Atazanavir tested positive in an in vitro clastogenicity test using primary human lymphocytes, in the absence and presence of metabolic activation. Atazanavir tested negative in the in vitro Ames reverse-mutation assay, in vivo micronucleus and DNA repair tests in rats, and in vivo DNA damage test in rat duodenum (comet assay).

Impairment of Fertility

At the systemic drug exposure levels (AUC) 0.9 (in male rats) or 2.3 (in female rats) times that of the human clinical dose, (300 mg/day atazanavir boosted with 100 mg/day ritonavir) significant effects on mating, fertility, or early embryonic development were not observed.

14 CLINICAL STUDIES

14.1 Adult Patients without Prior Antiretroviral Therapy

Study AI424-138: a 96-week study comparing the antiviral efficacy and safety of REYATAZ/ritonavir with lopinavir/ritonavir, each in combination with fixed-dose tenofovir-emtricitabine in HIV-1 infected treatment-naive subjects. Study AI424-138 was a 96-week, open-label, randomized, multicenter study, comparing REYATAZ (300 mg once daily) with ritonavir (100 mg once daily) to lopinavir with ritonavir (400/100 mg twice daily), each in combination with fixed-dose tenofovir with emtricitabine (300/200 mg once daily), in 878 antiretroviral treatment-naive treated patients. Patients had a mean age of 36 years (range: 19-72), 49% were Caucasian, 18% Black, 9% Asian, 23% Hispanic/Mestizo/mixed race, and 68% were male. The median baseline plasma CD4+ cell count was 204 cells/mm3 (range: 2 to 810 cells/mm3) and the mean baseline plasma HIV-1 RNA level was 4.94 log10 copies/mL (range: 2.60 to 5.88 log10 copies/mL). Treatment response and outcomes through Week 96 are presented in Table 26.

Table 26: Outcomes of Treatment Through Week 96 in Treatment-Naive Adults (Study AI424-138)
a As a fixed-dose combination: 300 mg tenofovir, 200 mg emtricitabine once daily.
b Patients achieved HIV RNA <50 copies/mL at Week 96. Roche Amplicor®, v1.5 ultra-sensitive assay.
c Pre-specified ITT analysis at Week 48 using as-randomized cohort: ATV/RTV 78% and LPV/RTV 76% (difference estimate: 1.7% [95% confidence interval: −3.8%, 7.1%]).
d Pre-specified ITT analysis at Week 96 using as-randomized cohort: ATV/RTV 74% and LPV/RTV 68% (difference estimate: 6.1% [95% confidence interval: 0.3%, 12.0%]).
e Includes viral rebound and failure to achieve confirmed HIV RNA <50 copies/mL through Week 96.
f Includes lost to follow-up, patient’s withdrawal, noncompliance, protocol violation, and other reasons.

REYATAZ
300 mg + ritonavir 100 mg
(once daily) with tenofovir/emtricitabine
(once daily)a
(n=441)

lopinavir
400 mg + ritonavir 100 mg
(twice daily) with tenofovir/emtricitabine
(once daily)a
(n=437)

Outcome

96 Weeks

96 Weeks

Responderb,c,d

75%

68%

Virologic failuree

17%

19%

Rebound

8%

10%

Never suppressed through Week 96

9%

9%

Death

1%

1%

Discontinued due to adverse event

3%

5%

Discontinued for other reasonsf

4%

7%

Through 96 weeks of therapy, the proportion of responders among patients with high viral loads (ie, baseline HIV RNA ≥100,000 copies/mL) was comparable for the REYATAZ/ritonavir (165 of 223 patients, 74%) and lopinavir/ritonavir (148 of 222 patients, 67%) arms. At 96 weeks, the median increase from baseline in CD4+ cell count was 261 cells/mm3 for the REYATAZ/ritonavir arm and 273 cells/mm3 for the lopinavir/ritonavir arm.

Study AI424-034: REYATAZ once daily compared to efavirenz once daily, each in combination with fixed-dose lamivudine + zidovudine twice daily. Study AI424-034 was a randomized, double-blind, multicenter trial comparing REYATAZ (400 mg once daily) to efavirenz (600 mg once daily), each in combination with a fixed-dose combination of lamivudine (3TC) (150 mg) and zidovudine (ZDV) (300 mg) given twice daily, in 810 antiretroviral treatment-naive patients. Patients had a mean age of 34 years (range: 18 to 73), 36% were Hispanic, 33% were Caucasian, and 65% were male. The mean baseline CD4+ cell count was 321 cells/mm3 (range: 64 to 1424 cells/mm3) and the mean baseline plasma HIV-1 RNA level was 4.8 log10 copies/mL (range: 2.2 to 5.9 log10 copies/mL). Treatment response and outcomes through Week 48 are presented in Table 27.

Table 27: Outcomes of Randomized Treatment Through Week 48 in Treatment-Naive Adults (Study AI424-034)
a Patients achieved and maintained confirmed HIV RNA <400 copies/mL (<50 copies/mL) through Week 48. Roche Amplicor® HIV-1 Monitor™ Assay, test version 1.0 or 1.5 as geographically appropriate.
b Includes viral rebound and failure to achieve confirmed HIV RNA <400 copies/mL through Week 48.
c Includes lost to follow-up, patient’s withdrawal, noncompliance, protocol violation, and other reasons.
d As a fixed-dose combination: 150 mg lamivudine, 300 mg zidovudine twice daily.

Outcome

REYATAZ
400 mg once daily
+ lamivudine
+ zidovudined
(n=405)

efavirenz
600 mg once daily
+ lamivudine
+ zidovudined
(n=405)

Respondera

67% (32%)

62% (37%)

Virologic failureb

20%

21%

Rebound

17%

16%

Never suppressed through Week 48

3%

5%

Death

–

<1%

Discontinued due to adverse event

5%

7%

Discontinued for other reasonsc

8%

10%

Through 48 weeks of therapy, the proportion of responders among patients with high viral loads (ie, baseline HIV RNA ≥100,000 copies/mL) was comparable for the REYATAZ and efavirenz arms. The mean increase from baseline in CD4+ cell count was 176 cells/mm3 for the REYATAZ arm and 160 cells/mm3for the efavirenz arm.

Study AI424-008: REYATAZ 400 mg once daily compared to REYATAZ 600 mg once daily, and compared to nelfinavir 1250 mg twice daily, each in combination with stavudine and lamivudine twice daily. Study AI424-008 was a 48-week, randomized, multicenter trial, blinded to dose of REYATAZ, comparing REYATAZ at two dose levels (400 mg and 600 mg once daily) to nelfinavir (1250 mg twice daily), each in combination with stavudine (40 mg) and lamivudine (150 mg) given twice daily, in 467 antiretroviral treatment-naive patients. Patients had a mean age of 35 years (range: 18 to 69), 55% were Caucasian, and 63% were male. The mean baseline CD4+ cell count was 295 cells/mm3 (range: 4 to 1003 cells/mm3) and the mean baseline plasma HIV-1 RNA level was 4.7 log10 copies/mL (range: 1.8 to 5.9 log10 copies/mL). Treatment response and outcomes through Week 48 are presented in Table 28.

Table 28: Outcomes of Randomized Treatment Through Week 48 in Treatment-Naive Adults (Study AI424-008)
a Patients achieved and maintained confirmed HIV RNA <400 copies/mL (<50 copies/mL) through Week 48. Roche Amplicor® HIV-1 Monitor™ Assay, test version 1.0 or 1.5 as geographically appropriate.
b Includes viral rebound and failure to achieve confirmed HIV RNA <400 copies/mL through Week 48.
c Includes lost to follow-up, patient’s withdrawal, noncompliance, protocol violation, and other reasons.

Outcome

REYATAZ
400 mg once daily +
lamivudine + stavudine
(n=181)

nelfinavir
1250 mg twice daily +
lamivudine + stavudine
(n=91)

Respondera

67% (33%)

59% (38%)

Virologic failureb

24%

27%

Rebound

14%

14%

Never suppressed through Week 48

10%

13%

Death

<1%

–

Discontinued due to adverse event

1%

3%

Discontinued for other reasonsc

7%

10%

Through 48 weeks of therapy, the mean increase from baseline in CD4+ cell count was 234 cells/mm3for the REYATAZ 400-mg arm and 211 cells/mm3 for the nelfinavir arm.

14.2 Adult Patients with Prior Antiretroviral Therapy

Study AI424-045: REYATAZ once daily + ritonavir once daily compared to REYATAZ once daily + saquinavir (soft gelatin capsules) once daily, and compared to lopinavir + ritonavir twice daily, each in combination with tenofovir + one NRTI. Study AI424-045 was a randomized, multicenter trial comparing REYATAZ (300 mg once daily) with ritonavir (100 mg once daily) to REYATAZ (400 mg once daily) with saquinavir soft gelatin capsules (1200 mg once daily), and to lopinavir + ritonavir (400/100 mg twice daily), each in combination with tenofovir and one NRTI, in 347 (of 358 randomized) patients who experienced virologic failure on HAART regimens containing PIs, NNRTIs, and NRTIs. The mean time of prior exposure to antiretrovirals was 139 weeks for PIs, 85 weeks for NNRTIs, and 283 weeks for NRTIs. The mean age was 41 years (range: 24 to 74); 60% were Caucasian, and 78% were male. The mean baseline CD4+ cell count was 338 cells/mm3 (range: 14 to 1543 cells/mm3) and the mean baseline plasma HIV-1 RNA level was 4.4 log10 copies/mL (range: 2.6 to 5.88 log10 copies/mL).

Treatment outcomes through Week 48 for the REYATAZ/ritonavir and lopinavir/ritonavir treatment arms are presented in Table 29. REYATAZ/ritonavir and lopinavir/ritonavir were similar for the primary efficacy outcome measure of time-averaged difference in change from baseline in HIV RNA level. Study AI424-045 was not large enough to reach a definitive conclusion that REYATAZ/ritonavir and lopinavir/ritonavir are equivalent on the secondary efficacy outcome measure of proportions below the HIV RNA lower limit of quantification [see MICROBIOLOGY, TABLES 24 AND 25 (12.4)].

Table 29: Outcomes of Treatment Through Week 48 in Study AI424-045 (Patients with Prior Antiretroviral Experience)
a Time-averaged difference through Week 48 for HIV RNA; Week 48 difference in HIV RNA percentages and CD4+ mean changes, REYATAZ/ritonavir vs lopinavir/ritonavir; CI = 97.5% confidence interval for change in HIV RNA; 95% confidence interval otherwise.
b Roche Amplicor® HIV-1 Monitor™ Assay, test version 1.5.
c Protocol-defined primary efficacy outcome measure.
d Based on patients with baseline and Week 48 CD4+ cell count measurements (REYATAZ/ritonavir, n=85; lopinavir/ritonavir, n=93).
e Patients achieved and maintained confirmed HIV-1 RNA <400 copies/mL (<50 copies/mL) through Week 48.

Outcome

REYATAZ 300 mg + ritonavir 100 mg once daily + tenofovir + 1 NRTI
(n=119)

lopinavir/ritonavir
(400/100 mg) twice daily
+ tenofovir + 1 NRTI

(n=118)

Differencea
(REYATAZ-lopinavir/ritonavir)
(CI)

HIV RNA Change from Baseline (log10copies/mL)b

−1.58

−1.70

+0.12c
(−0.17, 0.41)

CD4+ Change from Baseline (cells/mm3)d

116

123

−7
(−67, 52)

Percent of Patients Respondinge

HIV RNA <400 copies/mLb

55%

57%

−2.2%
(−14.8%, 10.5%)

HIV RNA <50 copies/mLb

38%

45%

−7.1%
(−19.6%, 5.4%)

No patients in the REYATAZ/ritonavir treatment arm and three patients in the lopinavir/ritonavir treatment arm experienced a new-onset CDC Category C event during the study.

In Study AI424-045, the mean change from baseline in plasma HIV-1 RNA for REYATAZ 400 mg with saquinavir (n=115) was −1.55 log10 copies/mL, and the time-averaged difference in change in HIV-1 RNA levels versus lopinavir/ritonavir was 0.33. The corresponding mean increase in CD4+ cell count was 72 cells/mm3. Through 48 weeks of treatment, the proportion of patients in this treatment arm with plasma HIV-1 RNA <400 (<50) copies/mL was 38% (26%). In this study, coadministration of REYATAZ and saquinavir did not provide adequate efficacy [see DRUG INTERACTIONS (7)].

Study AI424-045 also compared changes from baseline in lipid values. [See ADVERSE REACTIONS (6.1).]

Study AI424-043: Study AI424-043 was a randomized, open-label, multicenter trial comparing REYATAZ (400 mg once daily) to lopinavir/ritonavir (400/100 mg twice daily), each in combination with two NRTIs, in 300 patients who experienced virologic failure to only one prior PI-containing regimen. Through 48 weeks, the proportion of patients with plasma HIV-1 RNA <400 (<50) copies/mL was 49% (35%) for patients randomized to REYATAZ (n=144) and 69% (53%) for patients randomized to lopinavir/ritonavir (n=146). The mean change from baseline was −1.59 log10 copies/mL in the REYATAZ treatment arm and −2.02 log10 copies/mL in the lopinavir/ritonavir arm. Based on the results of this study, REYATAZ without ritonavir was inferior to lopinavir/ritonavir in PI-experienced patients with prior virologic failure and is not recommended for such patients.

14.3 Pediatric Patients

Pediatric Trials with REYATAZ Capsules

Assessment of the pharmacokinetics, safety, tolerability, and virologic response of REYATAZ capsules was based on data from the open-label, multicenter clinical trial PACTG 1020A which included patients from 6 years to 21 years of age. In this study, 105 patients (43 antiretroviral-naive and 62 antiretroviral-experienced) received once daily REYATAZ capsule formulation, with or without ritonavir, in combination with two NRTIs.

One-hundred five (105) patients (6 to less than 18 years of age) treated with the REYATAZ capsule formulation, with or without ritonavir, were evaluated. Using an ITT analysis, the overall proportions of antiretroviral-naive and -experienced patients with HIV RNA <400 copies/mL at Week 96 were 51% (22/43) and 34% (21/62), respectively. The overall proportions of antiretroviral-naive and -experienced patients with HIV RNA <50 copies/mL at Week 96 were 47% (20/43) and 24% (15/62), respectively. The median increase from baseline in absolute CD4 count at 96 weeks of therapy was 335 cells/mm3 in antiretroviral-naive patients and 220 cells/mm3 in antiretroviral-experienced patients.

Pediatric Trials with REYATAZ Oral Powder

Assessment of the pharmacokinetics, safety, tolerability, and virologic response of REYATAZ oral powder was based on data from two open-label, multicenter clinical trials.

•
AI424-397 (PRINCE I): In pediatric patients from 3 months to less than 6 years of age
•
AI424-451 (PRINCE II): In pediatric patients from 3 months to less than 11 years of age

In these studies 155 patients (59 antiretroviral-naive and 96 antiretroviral-experienced) received once daily REYATAZ oral powder and ritonavir, in combination with two NRTIs.

For inclusion in both trials, treatment-naive patients had to have genotypic sensitivity to REYATAZ and two NRTIs, and treatment-experienced patients had to have documented genotypic and phenotypic sensitivity at screening to REYATAZ and at least 2 NRTIs. Patients exposed only to antiretrovirals in utero or intrapartum were considered treatment-naive. Patients who received REYATAZ or REYATAZ/ritonavir at any time prior to study enrollment or who had a history of treatment failure on two or more protease inhibitors were excluded from the trials.

One hundred thirty-four (134) patients from both studies weighing 5 kg to less than 35 kg treated with REYATAZ oral powder with ritonavir were evaluated. Patients 5 kg to less than 10 kg received either 150 mg or 200 mg REYATAZ and 80 mg ritonavir oral solution; patients 10 kg to less than 15 kg received 200 mg REYATAZ and 80 mg ritonavir oral solution; patients 15 kg to less than 25 kg received 250 mg REYATAZ and 80 mg ritonavir oral solution; and patients 25 kg to less than 35 kg received 300 mg REYATAZ and 100 mg ritonavir.

Using a modified ITT analysis, the overall proportions of antiretroviral-naive and antiretroviral-experienced patients with HIV RNA <400 copies/mL at Week 48 were 79% (41/52) and 62% (51/82), respectively in patients who received REYATAZ oral powder with ritonavir. The overall proportions of antiretroviral-naive and antiretroviral-experienced patients with HIV RNA <50 copies/mL at Week 48 were 54% (28/52) and 50% (41/82), respectively in patients who received REYATAZ oral powder with ritonavir. The median increase from baseline in absolute CD4 count (percent) at 48 weeks of therapy (last observation carried forward) was 215 cells/mm3 (6%) in antiretroviral-naive patients and 133 cells/mm3 (4%) in antiretroviral-experienced patients who received REYATAZ oral powder with ritonavir.

16 HOW SUPPLIED/STORAGE AND HANDLING

REYATAZ Capsules

REYATAZ® (atazanavir) capsules are available in the following strengths and configurations of plastic bottles with child-resistant closures.

* 150 mg atazanavir equivalent to 170.8 mg atazanavir sulfate.
200 mg atazanavir equivalent to 227.8 mg atazanavir sulfate.
300 mg atazanavir equivalent to 341.69 mg atazanavir sulfate.

Product Strength*

Capsule Shell Color (cap/body)

Markings on Capsule
(ink color)

Capsules per Bottle

NDC Number

cap

body

150 mg

blue/powder blue

BMS 150 mg (white)

3624
(blue)

60

150 mg

200 mg

blue/blue

BMS 200 mg (white)

3631
(white)

60

200 mg

300 mg

red/blue

BMS 300 mg
(white)

3622
(white)

30

300 mg

Store REYATAZ capsules at 25°C (77°F); excursions permitted to 15°C-30°C (59°F-86°F) [see USP Controlled Room Temperature].

REYATAZ Oral Powder

REYATAZ oral powder is an orange-vanilla flavored powder, packed in child-resistant packets. Each packet contains 50 mg of atazanavir equivalent to 56.9 mg of atazanavir sulfate in 1.5 g of powder. REYATAZ oral powder is supplied in cartons (NDC 0003-3638-10) of 30 packets each. [See DOSAGE AND ADMINISTRATION (2.4).]

Store REYATAZ oral powder below 30°C (86°F). Once the REYATAZ oral powder is mixed with food or beverage, it may be kept at room temperature 20°C to 30°C (68°F-86°F) for up to 1 hour prior to administration. Store REYATAZ oral powder in the original packet and do not open until ready to use.

17 PATIENT COUNSELING INFORMATION

Advise the patient to read the FDA-approved patient labeling (PATIENT INFORMATION and INSTRUCTIONS FOR USE).

REYATAZ is not a cure for HIV infection and patients may continue to experience illnesses associated with HIV infection, including opportunistic infections. Tell patients that sustained decreases in plasma HIV RNA have been associated with a reduced risk of progression to AIDS and death. Advise patients to remain under the care of a healthcare provider while using REYATAZ.

HIV Transmission

Advise patients to avoid doing things that can spread HIV infection to others.

•
Do not share or reuse needles or other injection equipment.
•
Do not share personal items that can have blood or body fluids on them, like toothbrushes and razor blades.
•
Do not have any kind of sex without protection. Always practice safer sex by using a latex or polyurethane condom to lower the chance of sexual contact with semen, vaginal secretions, or blood.
•
Do not breastfeed. REYATAZ can be passed to your baby in your breast milk and it is not known whether it could harm your baby. Also, mothers with HIV should not breastfeed because HIV can be passed to the baby in breast milk.

Cardiac Conduction Abnormalities

Inform patients that atazanavir may produce changes in the electrocardiogram (eg, PR prolongation). Tell patients to consult their healthcare provider if they are experiencing symptoms such as dizziness or lightheadedness [see WARNINGS AND PRECAUTIONS (5.1)].

Severe Skin Reaction

Inform patients that there have been reports of severe skin reactions (eg, Stevens-Johnson syndrome, erythema multiforme, and toxic skin eruptions) with REYATAZ use. Advise patients that if signs or symptoms of severe skin reactions or hypersensitivity reactions develop, they must discontinue REYATAZ and seek medical evaluation immediately [see WARNINGS AND PRECAUTIONS (5.2) and ADVERSE REACTIONS (6.1)].

Hyperbilirubinemia

Inform patients that asymptomatic elevations in indirect bilirubin have occurred in patients receiving REYATAZ. This may be accompanied by yellowing of the skin or whites of the eyes and alternative antiretroviral therapy may be considered if the patient has cosmetic concerns [see WARNINGS AND PRECAUTIONS (5.3)].

Patients with Phenylketonuria

Advise caregivers of patients with phenylketonuria that REYATAZ oral powder contains phenylalanine [see WARNINGS AND PRECAUTIONS (5.4)].

Nephrolithiasis and Cholelithiasis

Inform patients that kidney stones and/or gallstones have been reported with REYATAZ use. Some patients with kidney stones and/or gallstones required hospitalization for additional management and some had complications. Discontinuation of REYATAZ may be necessary as part of the medical management of these adverse events [see WARNINGS AND PRECAUTIONS (5.6)].

Drug Interactions

REYATAZ may lead to significant interaction with some drugs; therefore, advise patients to report the use of any other prescription, nonprescription medication, or herbal products, particularly St. John’s wort, to their healthcare provider prior to use [see CONTRAINDICATIONS (4), WARNINGS AND PRECAUTIONS (5.7)].

Fat Redistribution

Inform patients that redistribution or accumulation of body fat may occur in patients receiving antiretroviral therapy including protease inhibitors and that the cause and long-term health effects of these conditions are not known at this time.

Dosing Instructions

Advise patients to take REYATAZ with food every day and take other concomitant antiretroviral therapy as prescribed. REYATAZ must always be used in combination with other antiretroviral drugs. Advise patients that they should not alter the dose or discontinue therapy without consulting with their healthcare provider. Tell patients if a dose of REYATAZ is missed, they should take the dose as soon as possible and then return to their normal schedule; however, if a dose is skipped the patient should not double the next dose.

Pregnancy

Inform pregnant patients that there is a pregnancy exposure registry that monitors pregnancy outcomes in women exposed to REYATAZ during pregnancy. Healthcare providers are encouraged to register patients by calling the Antiretroviral Pregnancy Registry [see USE IN SPECIFIC POPULATIONS (8.1)].

PATIENT PACKAGE INSERT

PATIENT INFORMATION

REYATAZ® (RAY-ah-taz)
(atazanavir)
capsules

REYATAZ® (RAY-ah-taz)
(atazanavir)
oral powder

Important: Ask your healthcare provider or pharmacist about medicines that should not be taken with REYATAZ. For more information, see “Who should not take REYATAZ?” and “What should I tell my healthcare provider before taking REYATAZ?”

What is REYATAZ?

REYATAZ is a prescription HIV-1 (Human Immunodeficiency Virus-type 1) medicine that is used with other antiretroviral medicines to treat HIV-1 infection in adults and children 3 months of age and older and who weigh at least 11 pounds (5 kg). HIV-1 is the virus that causes AIDS (Acquired Immunodeficiency Syndrome).

REYATAZ should not be used in children younger than 3 months of age.

When used with other antiretroviral medicines to treat HIV-1 infection, REYATAZ may help:

•
reduce the amount of HIV-1 in your blood. This is called “viral load”.
•
increase the number of CD4+ (T) cells in your blood that help fight off other infections.

Reducing the amount of HIV-1 and increasing the CD4+ (T) cells in your blood may help improve your immune system. This may reduce your risk of death or getting infections that can happen when your immune system is weak (opportunistic infections).

REYATAZ does not cure HIV-1 infection or AIDS. You must keep taking HIV-1 medicines to control HIV-1 infection and decrease HIV-related illnesses.

Avoid doing things that can spread HIV-1 infection to others:

•
Do not share or reuse needles or other injection equipment.
•
Do not share personal items that can have blood or body fluids on them, like toothbrushes and razor blades.
•
Do not have any kind of sex without protection. Always practice safer sex by using a latex or polyurethane condom to lower the chance of sexual contact with any body fluids such as semen, vaginal secretions, or blood.

Ask your healthcare provider if you have any questions about how to prevent passing HIV-1 to other people.

Who should not take REYATAZ?

Do not take REYATAZ if you:

•
are allergic to atazanavir or any of the ingredients in REYATAZ. See the end of this leaflet for a complete list of ingredients in REYATAZ.
•
are taking any of the following medicines. Taking REYATAZ with these medicines may affect how REYATAZ works. REYATAZ may cause serious life-threatening side effects or death when used with these medicines:

o
alfuzosin (UROXATRAL ®)
o
cisapride (PROPULSID ®)
o
ergot medicines including:

▪
ergotamine tartrate (CAFERGOT ®, MIGERGOT ®, ERGOMAR ®, ERGOSTAT ®, MEDIHALER ®, Ergotamine, WIGRAINE ®, WIGRETTES ®)
▪
dihydroergotamine mesylate (D.H.E. 45 ®, MIGRANAL ®)
▪
methylergonovine (METHERGINE ®)

o
indinavir (CRIXIVAN ®)
o
irinotecan (CAMPTOSAR ®)
o
lurasidone (LATUDA ®) if REYATAZ is used with ritonavir (NORVIR ®)

o
lovastatin (ADVICOR ®, ALTOPREV ®, MEVACOR ®)
o
midazolam (VERSED ®), when taken by mouth for sedation
o
nevirapine (VIRAMUNE ®, VIRAMUNE XR ®)
o
pimozide (ORAP ®)
o
rifampin (RIFADIN ®, RIFAMATE®, RIFATER ®, RIMACTANE ®)
o
sildenafil (REVATIO ®), when used for the treatment of pulmonary arterial hypertension
o
simvastatin (SIMCOR ®, VYTORIN ®, ZOCOR ®)
o
St. John’s wort (Hypericum perforatum)
o
triazolam (HALCION ®)

Serious problems can happen if you or your child takes any of the medicines listed above with REYATAZ.

What should I tell my healthcare provider before taking REYATAZ?

Before taking REYATAZ, tell your healthcare provider if you:

•
have heart problems
•
have liver problems, including hepatitis B or C virus infection
•
have phenylketonuria (PKU). REYATAZ oral powder contains phenylalanine as part of the artificial sweetener aspartame. The artificial sweetener can be harmful to people with PKU.
•
are receiving dialysis treatment
•
have diabetes
•
have hemophilia
•
have any other medical conditions
•
are pregnant or plan to become pregnant. Talk to your healthcare provider about taking REYATAZ during your pregnancy or if you are planning to become pregnant while you are taking REYATAZ.

o
Hormonal forms of birth control, such as injections, vaginal rings or implants, contraceptive patch, and some birth control pills may not work during treatment with REYATAZ. Talk to your healthcare provider about forms of birth control that may be used during treatment with REYATAZ.
o
Pregnancy Registry. There is a pregnancy registry for women who take antiretroviral medicines during pregnancy. The purpose of this registry is to collect information about the health of you and your baby. Talk to your healthcare provider about how you can take part in this registry.
o
After your baby is born, tell your healthcare provider if your baby’s skin or the white part of the eyes turns yellow.

•
are breastfeeding or plan to breastfeed. Do not breastfeed if you are taking REYATAZ. You should not breastfeed if you have HIV-1 because of the risk of passing HIV-1 to your baby. REYATAZ can pass into your breast milk. Talk to your healthcare provider about the best way to feed your baby.

Tell your healthcare provider about all the medicines you take, including prescription and over-the-counter medicines, vitamins, and herbal supplements.

Some medicines interact with REYATAZ. Keep a list of your medicines to show your healthcare provider and pharmacist. You can ask your healthcare provider or pharmacist for a list of medicines that interact with REYATAZ. Do not start taking a new medicine without telling your healthcare provider. Your healthcare provider can tell you if it is safe to take REYATAZ with other medicines.

How should I take REYATAZ?

•
Take REYATAZ exactly as your healthcare provider tells you to.
•
Do not change your dose or stop taking REYATAZ unless your healthcare provider tells you to.
•
Stay under the care of your healthcare provider during treatment with REYATAZ.
•
REYATAZ must be used with other antiretroviral medicines.
•
Take REYATAZ 1 time each day.
•
REYATAZ comes as capsules and oral powder.
•
Take REYATAZ capsules and oral powder with food.
•
Swallow the capsules whole. Do not open the capsules.
•
REYATAZ oral powder must be mixed with food or liquid. Your child’s healthcare provider will prescribe the right dose of REYATAZ based on your child’s weight.
•
REYATAZ oral powder must be taken with ritonavir.
•
If you miss a dose of REYATAZ, take it as soon as you remember. Then take the next dose at your regular time. Do not take 2 doses at the same time.
•
If you take too much REYATAZ, call your healthcare provider or go to the nearest hospital emergency room right away.

When your supply of REYATAZ starts to run low, get more from your healthcare provider or pharmacy. It is important not to run out of REYATAZ. The amount of HIV-1 in your blood may increase if the medicine is stopped for even a short time. The virus may become resistant to REYATAZ and harder to treat.

What are the possible side effects of REYATAZ?

REYATAZ can cause serious side effects, including:

•
A change in the way your heart beats (heart rhythm change). Tell your healthcare provider right away if you get dizzy or lightheaded. These could be symptoms of a heart problem.
•
Skin rash. Skin rash is common with REYATAZ but can sometimes be severe. Skin rash usually goes away within 2 weeks without any change in treatment. Severe rash may develop in association with other symptoms which could be serious. If you develop a severe rash or a rash with any of the following symptoms, stop taking REYATAZ and call your healthcare provider right away:

o
general feeling of discomfort or “flu-like” symptoms
o
fever
o
muscle or joint aches
o
red or inflamed eyes, like “pink eye” (conjunctivitis)

o
blisters
o
mouth sores
o
swelling of your face
o
painful, warm, or red lump under your skin

•
Yellowing of your skin or the white part of your eyes is common with REYATAZ, and is usually not harmful in adults and infants older than 3 months of age; but it could also be a symptom of a serious problem. These effects may be due to increases in bilirubin levels in your blood (bilirubin is made by the liver). Although these effects may not be damaging to your liver, skin, or eyes, tell your healthcare provider right away if your skin or the white part of your eyes turns yellow.
•
Liver problems. If you have liver problems, including hepatitis B or C infection, your liver problems may get worse when you take REYATAZ. Your healthcare provider will do blood tests to check your liver before you start REYATAZ and during treatment. Tell your healthcare provider right away if you get any of the following symptoms:

o
dark “tea-colored” urine
o
your skin or the white part of your eyes turns yellow
o
light colored stools
o
nausea

o
itching
o
stomach-area pain

•
Kidney stones have happened in some people who take REYATAZ. Tell your healthcare provider right away if you get symptoms of kidney stones which may include, pain in your low back or low stomach-area, blood in your urine, or pain when you urinate.
•
Gallbladder problems have happened in some people who take REYATAZ. Tell your healthcare provider right away if you get symptoms of gallbladder problems which may include:

o
pain in the right or middle upper stomach area
o
fever

o
nausea and vomiting
o
your skin or the white part of your eyes turns yellow

•
Diabetes and high blood sugar (hyperglycemia) have happened or have worsened in some people who take protease inhibitor medicines like REYATAZ. Some people have had to start taking medicine to treat diabetes or have had to change their diabetes medicine.
•
Changes in your immune system (Immune Reconstitution Syndrome) can happen when you start taking HIV-1 medicines. Your immune system may get stronger and begin to fight infections that have been hidden in your body for a long time. Tell your healthcare provider if you start having new symptoms after starting REYATAZ.
•
Changes in body fat can happen in people taking HIV-1 medicines. These changes may include increased amount of fat in the upper back and neck (“buffalo hump”), breast, and around the main part of your body (trunk). Loss of fat from the legs, arms, and face may also happen. The exact cause and long-term health effects of these conditions are not known.
•
Increased bleeding problems in people with hemophilia have happened when taking protease inhibitors like REYATAZ.

The most common side effects of REYATAZ include:

•
nausea
•
headache
•
stomach-area pain
•
vomiting
•
trouble sleeping
•
numbness, tingling, or burning of hands or feet

•
dizziness
•
muscle pain
•
diarrhea
•
depression
•
fever

Tell your healthcare provider if you have any side effect that bothers you or that does not go away.

These are not all the possible side effects of REYATAZ. For more information, ask your healthcare provider or pharmacist.

Call your doctor for medical advice about side effects. You may report side effects to FDA at 1-800-FDA-1088.

How should I store REYATAZ?

REYATAZ capsules:

•
Store REYATAZ capsules at room temperature, between 68°F to 77°F (20°C to 25°C).
•
Keep capsules in a tightly closed container.

REYATAZ oral powder:

•
Store REYATAZ oral powder below 86°F (30°C).
•
Store REYATAZ oral powder in the original packet. Do not open until ready to use.
•
After REYATAZ oral powder is mixed with food or liquid it may be kept at room temperature 68°F to 86°F (20°C to 30°C) for up to 1 hour. Take REYATAZ oral powder within 1 hour after mixing with food or liquid.

Keep REYATAZ and all medicines out of the reach of children.

General information about the safe and effective use of REYATAZ

Medicines are sometimes prescribed for purposes other than those listed in a Patient Information leaflet. Do not use REYATAZ for a condition for which it was not prescribed. Do not give REYATAZ to other people, even if they have the same symptoms that you have. It may harm them. If you would like more information, talk with your healthcare provider. You can ask your pharmacist or healthcare provider for information about REYATAZ that is written for health professionals.

For more information, go to www.reyataz.com or call 1-800-321-1335.

What are the ingredients in REYATAZ?

Active ingredient: atazanavir sulfate

Inactive ingredients:

REYATAZ capsules: crospovidone, lactose monohydrate, and magnesium stearate. The capsule shells contain gelatin, FD&C Blue No. 2, titanium dioxide, black iron oxide, red iron oxide, and yellow iron oxide. The capsules are printed with ink containing shellac, titanium dioxide, FD&C Blue No. 2, isopropyl alcohol, ammonium hydroxide, propylene glycol, n-butyl alcohol, simethicone, and dehydrated alcohol.

REYATAZ oral powder: aspartame, sucrose, and orange-vanilla flavor.

Distributed by:

Bristol-Myers Squibb Company, Princeton, NJ 08543 USA.

Product of Ireland

REYATAZ® is a registered trademark of Bristol-Myers Squibb Company. Other brands listed are the trademarks of their respective owners and are not trademarks of Bristol-Myers Squibb Company.

This Patient Information has been approved by the U.S. Food and Drug Administration.

Revised: September 2016

INSTRUCTIONS FOR USE

REYATAZ® (RAY-ah-taz)
(atazanavir)
oral powder

Read this Instructions for Use before you prepare your child’s first dose of REYATAZ oral powder, each time you get a refill, and as needed. There may be new information. This information does not take the place of talking to your child’s healthcare provider about their medical condition or treatment. Ask your child’s healthcare provider or pharmacist if you have questions about how to mix or give a dose of REYATAZ oral powder.

Important information:

•
For more information about REYATAZ oral powder, see the Patient Information leaflet.
•
REYATAZ oral powder must be mixed with food or liquid. If REYATAZ oral powder is mixed with water, the child must eat food right after taking REYATAZ oral powder.
•
REYATAZ oral powder must be taken with ritonavir.
•
Talk with your child’s healthcare provider to help decide the best schedule for giving your child REYATAZ oral powder.

Instructions for mixing REYATAZ oral powder:

REYATAZ oral powder should be mixed with food such as applesauce or yogurt, instead of a liquid (milk, infant formula, or water) in young children and infants who can take food.

•
Infants less than 6 months old and who cannot eat solid food or drink from a cup should be given REYATAZ oral powder mixed with infant formula using an oral dosing syringe.
•
REYATAZ oral powder that is mixed in infant formula or liquid should not be given using a baby bottle.

When preparing REYATAZ oral powder with either food or liquid, choose a clean, flat work surface. Place a clean paper towel on the work surface. Place the supplies you will need on the paper towel.

Wash and dry your hands before and after preparing REYATAZ oral powder.

Preparing a dose of REYATAZ oral powder mixed with food:

Before you prepare a dose of REYATAZ oral powder mixed with food, gather the following supplies:

•
paper towel
•
tablespoon
•
small clean container (such as a small cup or bowl)
•
a food such as applesauce or yogurt
•
the correct number of packets of REYATAZ oral powder needed for the prescribed dose

Step 1. Place at least 1 tablespoon of a food such as applesauce or yogurt in the small container (see Figure A).

[Reyataz Figure A]

Figure A

Step 2. Tap the packet of REYATAZ oral powder to settle the contents to the bottom of the packet (see Figure B).

[Reyataz Figure B]

Figure B

Step 3. Using a clean pair of scissors, cut open the packet on the dotted line (see Figure C).

[Reyataz Figure C]

Figure C

Step 4. Empty the contents of the packet into the small container onto the food (see Figure D).

[Reyataz Figure D]

Figure D

Repeat Steps 2 through 4 for each packet of REYATAZ oral powder needed for the total prescribed dose.

Step 5. Use a tablespoon to gently mix the powder and the food together (see Figure E).

[Reyataz Figure E]

Figure E

Steps 6 through 8 must be completed within 1 hour of mixing the medicine.

Step 6. Use the tablespoon or a small spoon to feed the REYATAZ oral powder and food mixture to your child. Look in your child’s mouth to make sure that all of the mixture is swallowed.

Step 7. Add 1 tablespoon more of food to the empty container and gently stir to mix with any contents that may still be in the container.

Step 8. Use the tablespoon or a small spoon to feed your child the mixture, making sure your child has swallowed all of the mixture.

Step 9. Give your child ritonavir as prescribed right after taking REYATAZ oral powder.

Step 10. Wash the container and tablespoon. Allow the container and spoon to dry. Throw away the paper towel and clean the work surface.

Preparing a dose of REYATAZ oral powder mixed with liquid in a small drinking cup:

Before you prepare a dose of REYATAZ oral powder mixed with liquid in a small drinking cup, gather the following supplies:

•
paper towel
•
spoon
•
30 milliliter (mL) medicine cup (ask your pharmacist for this). See Figure F.
•
small drinking cup
•
liquid such as milk or water
•
the correct number of packets of REYATAZ oral powder needed for the prescribed dose

[Reyataz Figure F]

Figure F

Step 1. Using the 30 mL medicine cup, pour at least 30 mL of liquid into the small drinking cup (see Figure G).

[Reyataz Figure G]

Figure G

Step 2. Tap the packet of REYATAZ oral powder to settle the contents to the bottom of the packet (see Figure H).

[Reyataz Figure H]

Figure H

Step 3. Using a clean pair of scissors, cut open the packet on the dotted line (see Figure I).

[Reyataz Figure I]

Figure I

Step 4. Empty the contents of the packet into the small drinking cup (see Figure J).

[Reyataz Figure J]

Figure J

Repeat Steps 2 through 4 for each packet of REYATAZ oral powder needed for the total prescribed dose.

Step 5. Hold the small drinking cup with one hand. With your other hand, use the spoon to gently mix the powder and the liquid (see Figure K).

[Reyataz Figure K]

Figure K

Steps 6 and 7 must be completed within 1 hour of mixing the medicine.

Step 6. Have your child drink all of the mixture in the small drinking cup.

Step 7. To make sure there is no mixture left in the small drinking cup add 15 mL more liquid to the small drinking cup:

•
Stir with the spoon.
•
Repeat Step 6 above.

If REYATAZ oral powder is mixed with water, your child must eat food right after taking REYATAZ oral powder.

Step 8. Give your child ritonavir as prescribed right after taking REYATAZ oral powder.

Step 9. Wash the small drinking cup, medicine cup, and spoon. Allow the small drinking cup, medicine cup, and spoon to dry. Throw away the paper towel and clean the work surface.

Preparing a dose of REYATAZ oral powder mixed with liquid infant formula using an oral dosing syringe and a small medicine cup:

Before you prepare a dose of REYATAZ oral powder mixed with infant formula using an oral dosing syringe, gather the following supplies:

•
paper towel
•
small spoon
•
30 milliliter (mL) medicine cup (ask your pharmacist for this). See Figure L.
•
10 mL oral dosing syringe (ask your pharmacist for this). See Figure L.
•
infant formula
•
the correct number of packets of REYATAZ oral powder needed for the prescribed dose

[Reyataz Figure L]

Figure L

Step 1. Prepare the infant formula according to the directions on the infant formula package.

Step 2. Pour 10 mL of infant formula into the medicine cup (see Figure M).

[Reyataz Figure M]

Figure M

Step 3. Tap the packet of REYATAZ oral powder to settle the contents to the bottom of the packet (see Figure N).

[Reyataz Figure N]

Figure N

Step 4. Using a clean pair of scissors, cut open the packet on the dotted line (see Figure O).

[Reyataz Figure O]

Figure O

Step 5. Empty the contents of the packet into the medicine cup (see Figure P).

[Reyataz Figure P]

Figure P

Repeat Steps 3 through 5 for each packet of REYATAZ oral powder needed for the total prescribed dose.

Step 6. Hold the medicine cup with one hand. With your other hand, use the small spoon to gently mix the powder and the infant formula (see Figure Q).

[Reyataz Figure Q]

Figure Q

Steps 7 through 9 must be completed within 1 hour of mixing the medicine.

Step 7. Draw up the powder and infant formula mixture into the oral dosing syringe as follows:

•
Check that the plunger is completely pushed into barrel of the syringe (see Figure R).

[Reyataz Figure R]

Figure R

•
Place the tip of the syringe into the powder and infant formula mixture in the medicine cup (see Figure S).

[Reyataz Figure S]

Figure S

•
Slowly pull back on the plunger and draw up 10 mL of the mixture (see Figure T).

[Reyataz Figure T]

Figure T

Step 8. Place the tip of the oral dosing syringe in your baby’s mouth along the inner cheek on either the right or left side (see Figure U). Slowly push on the plunger to give your baby all of the REYATAZ oral powder and infant formula mixture.

•
Draw up any remaining mixture with the oral dosing syringe and repeat until all of the mixture has been given to the baby.

[Reyataz Figure U]

Figure U

Step 9. To make sure there is no mixture left in the medicine cup or syringe:

•
Repeat Step 1 above to add 10 mL more infant formula to the medicine cup
•
Stir with a small spoon.
•
Then repeat Steps 7 through 8 above.

To make sure that your baby gets all of the medicine, do not give REYATAZ oral powder in a baby bottle.

Step 10. Give your baby ritonavir as prescribed right after taking REYATAZ oral powder.

Step 11. Remove the plunger from the oral dosing syringe. Wash the medicine cup, spoon, and oral dosing syringe. Allow the medicine cup, spoon, and oral dosing syringe to dry. Throw away the paper towel and clean the work surface.

How should I store REYATAZ oral powder?

•
Store REYATAZ oral powder below 86°F (30°C).
•
Store REYATAZ oral powder in the original packet. Do not open until ready to use.
•
After REYATAZ oral powder is mixed with food or liquid, it may be kept at room temperature 68°F to 86°F (20°C to 30°C) for up to 1 hour. Take REYATAZ oral powder within 1 hour after mixing with food or liquid.
Keep REYATAZ oral powder and all medicines out of the reach of children.
This Instructions for Use has been approved by the U.S. Food and Drug Administration.

Distributed by:
Bristol-Myers Squibb Company
Princeton, NJ 08543 USA

Product of Ireland

Revised: September 2016